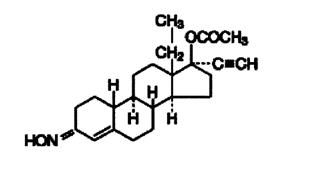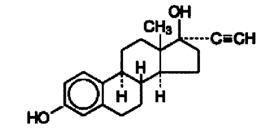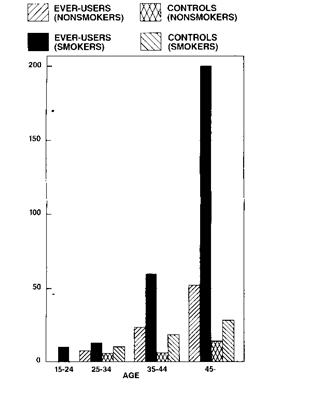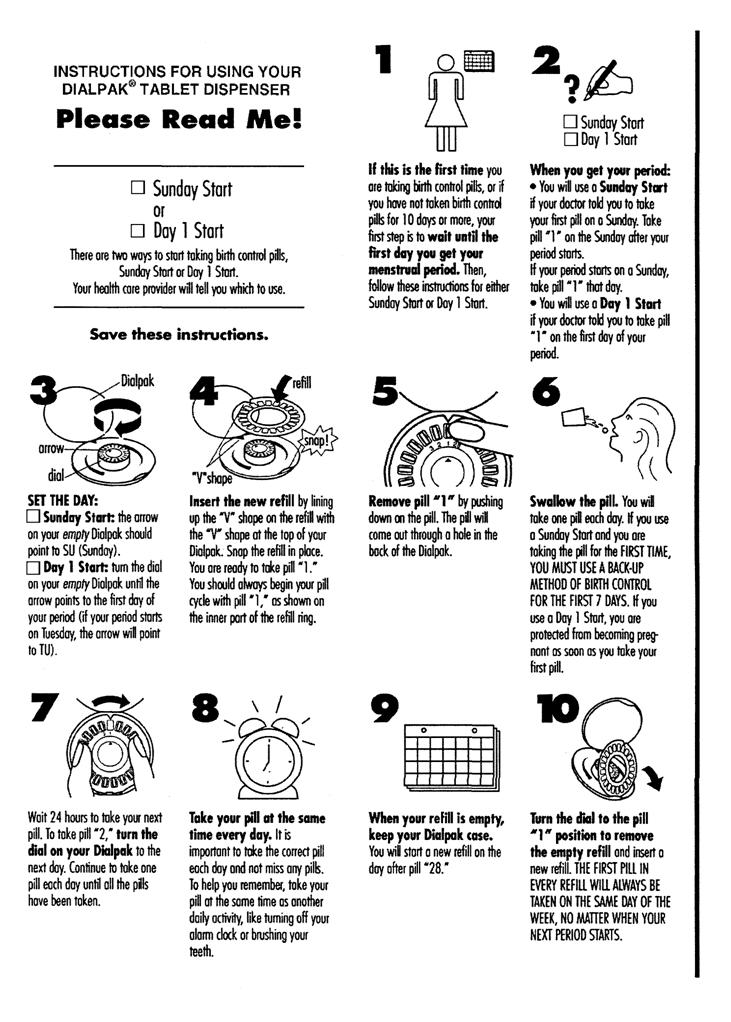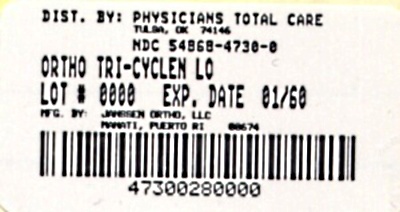 DRUG LABEL: ORTHO TRI CYCLEN Lo
NDC: 54868-4730 | Form: KIT | Route: ORAL
Manufacturer: Physicians Total Care, Inc.
Category: prescription | Type: HUMAN PRESCRIPTION DRUG LABEL
Date: 20110203

ACTIVE INGREDIENTS: norgestimate 0.18 mg/1 1; ethinyl estradiol 0.025 mg/1 1; norgestimate 0.215 mg/1 1; ethinyl estradiol 0.025 mg/1 1; norgestimate 0.25 mg/1 1; ethinyl estradiol 0.025 mg/1 1
INACTIVE INGREDIENTS: Carnauba Wax; Croscarmellose Sodium; Hypromelloses; Lactose; Magnesium Stearate; Cellulose, Microcrystalline; Polyethylene Glycol; Titanium Dioxide; Water; FD&C Blue No. 2; Aluminum Oxide; Carnauba Wax; Croscarmellose Sodium; Hypromelloses; Lactose; Magnesium Stearate; Cellulose, Microcrystalline; Polyethylene Glycol; Titanium Dioxide; Water; FD&C Blue No. 2; Aluminum Oxide; Carnauba Wax; Croscarmellose Sodium; Hypromelloses; Lactose; Magnesium Stearate; Cellulose, Microcrystalline; Polyethylene Glycol; Polysorbate 80; Titanium Dioxide; Water; FD&C Blue No. 2; Aluminum Oxide; Ferric Oxide Red; Hypromelloses; Lactose; Magnesium Stearate; Polyethylene Glycol; Starch, Corn; Talc; Titanium Dioxide; Water

ORTHO TRI-CYCLEN® Lo Tablets
(norgestimate/ethinyl estradiol)

Patients should be counseled that this product does not protect against HIV infection (AIDS) and other sexually transmitted diseases.

DESCRIPTION

ORTHO TRI-CYCLEN® Lo Tablets is a combination oral contraceptive containing the progestational compound norgestimate and the estrogenic compound ethinyl estradiol.

ORTHO TRI-CYCLEN® Lo Tablets

Each white tablet contains 0.180 mg of the progestational compound, norgestimate (+)-13-Ethyl-17-hydroxy-18, 19-dinor-17α-pregn-4-en-20-yn-3-one oxime acetate (ester) and 0.025 mg of the estrogenic compound, ethinyl estradiol (19-nor-17α-pregna,1,3,5(10)-trien-20-yne-3,17-diol). Inactive ingredients include lactose, magnesium stearate, croscarmellose sodium, microcrystalline cellulose, carnauba wax, hypromellose, polyethylene glycol, titanium dioxide, and purified water.

Each light blue tablet contains 0.215 mg of the progestational compound norgestimate (+)-13-Ethyl-17-hydroxy-18, 19-dinor-17α-pregn-4-en-20-yn-3-one oxime acetate (ester) and 0.025 mg of the estrogenic compound, ethinyl estradiol (19-nor-17α-pregna,1,3,5(10)-trien-20-yne-3,17-diol). Inactive ingredients include FD & C Blue No. 2 Aluminum Lake, lactose, magnesium stearate, croscarmellose sodium, microcrystalline cellulose, carnauba wax, hypromellose, polyethylene glycol, titanium dioxide, and purified water.

Each dark blue tablet contains 0.250 mg of the progestational compound norgestimate (+)-13-Ethyl-17-hydroxy-18, 19-dinor-17α-pregn-4-en-20-yn-3-one oxime acetate (ester) and 0.025 mg of the estrogenic compound, ethinyl estradiol (19-nor-17α-pregna,1,3,5(10)-trien-20-yne-3,17-diol). Inactive ingredients include FD & C Blue No. 2 Aluminum Lake, lactose, magnesium stearate, croscarmellose sodium, microcrystalline cellulose, polysorbate 80, carnauba wax, hypromellose, polyethylene glycol, titanium dioxide, and purified water.

Each dark green tablet contains only inert ingredients, as follows: FD & C Blue No. 2 Aluminum Lake, lactose, magnesium stearate, pregelatinized starch, ferric oxide, hypromellose, polyethylene glycol, titanium dioxide, talc and purified water.

Norgestimate

Ethinyl Estradiol

CLINICAL PHARMACOLOGY

Oral Contraception

Combination oral contraceptives act by suppression of gonadotropins. Although the primary mechanism of this action is inhibition of ovulation, other alterations include changes in the cervical mucus (which increase the difficulty of sperm entry into the uterus) and the endometrium (which reduce the likelihood of implantation).

Receptor binding studies, as well as studies in animals and humans, have shown that norgestimate and 17-deacetyl norgestimate, the major serum metabolite, combine high progestational activity with minimal intrinsic androgenicity.^90–93 Norgestimate, in combination with ethinyl estradiol, does not counteract the estrogen-induced increases in sex hormone binding globulin (SHBG), resulting in lower serum testosterone.^90,91,94

PHARMACOKINETICS

Absorption

Norgestimate (NGM) and ethinyl estradiol (EE) are rapidly absorbed following oral administration. Norgestimate is rapidly and completely metabolized by first-pass (intestinal and/or hepatic) mechanisms to norelgestromin (NGMN) and norgestrel (NG), which are the major active metabolites of norgestimate. Mean pharmacokinetic parameters for NGMN, NG and EE during three cycles of administration of ORTHO TRI-CYCLEN® Lo are summarized in Table 1. These results indicate that: (1) Peak serum concentrations of NGMN and EE were generally reached by 2 hours after dosing; (2) Accumulation following multiple dosing of the 180 mcg NGM / 25 mcg dose is approximately 1.5 to 2 fold for NGMN and approximately 1.5 fold for EE compared with single dose administration, in agreement with that predicted based on linear kinetics of NGMN and EE; (3) The kinetics of NGMN are dose proportional following NGM doses of 180 to 250 mcg; (4) Steady-state conditions for NGMN following each NGM dose and for EE were achieved during the three cycle study; (5) Non-linear accumulation (4.5–14.5 fold) of norgestrel was observed as a result of high affinity binding to SHBG, which limits its biological activity.^100 The effect of food on the pharmacokinetics of ORTHO TRI-CYCLEN® Lo has not been studied.

Table 1 provides a summary of norelgestromin, norgestrel and ethinyl estradiol pharmacokinetic parameters.

Table 1: Mean (SD) Pharmacokinetic Parameters of ORTHO TRI-CYCLEN® Lo During a Three Cycle Study
Analyte^1 | Cycle | Day | Cmax | tmax (h) | AUC0–24h | t1/2 (h)
NGMN(2–4) | 1 | 1 | 0.91 (0.27) | 1.8 (1.0) | 5.86 (1.54) | NC
 | 3 | 7 | 1.42 (0.43) | 1.8 (0.7) | 11.3 (3.2) | NC
 |  | 14 | 1.57 (0.39) | 1.8 (0.7) | 13.9 (3.7) | NC
 |  | 21 | 1.82 (0.54) | 1.5 (0.7) | 16.1 (4.8) | 28.1(10.6)
NG(2–4) | 1 | 1 | 0.32 (0.14) | 2.0 (1.1) | 2.44 (2.04) | NC
 | 3 | 7 | 1.64 (0.89) | 1.9 (0.9) | 27.9 (18.1) | NC
 |  | 14 | 2.11 (1.13) | 4.0 (6.3) | 40.7 (24.8) | NC
 |  | 21 | 2.79 (1.42) | 1.7 (1.2) | 49.9 (27.6) | 36.4 (10.2)
EE(2,3,5) | 1 | 1 | 55.6 (18.1) | 1.7 (0.5) | 421 (118) | NC
 | 3 | 7 | 91.1 (36.7) | 1.3 (0.3) | 782 (329) | NC
 |  | 14 | 96.9 (38.5) | 1.3 (0.3) | 796 (273) | NC
 |  | 21 | 95.9 (38.9) | 1.3 (0.6) | 771 (303) | 17.7(4.4)
^1 NGMN = Norelgestromin, NG = norgestrel, EE = ethinyl estradiol
^2 Cmax = peak serum concentration, tmax = time to reach peak serum concentration, AUC0–24h = area under serum concentration vs. time curve from 0 to 24 hours, t1/2 = elimination half-life.
^3 units for all analytes; h = hours
^4 units for NGMN and NG – Cmax = ng/mL, AUC0–24h = h.ng/mL
^5 units for EE only – Cmax = pg/mL, AUC0–24h = h.pg/mL
NC = not calculated

Distribution

Norelgestromin and norgestrel (a serum metabolite of norelgestromin) are highly bound (>97%) to serum proteins. Norelgestromin is bound to albumin and not to SHBG, while norgestrel is bound primarily to SHBG. Ethinyl estradiol is extensively bound (>97%) to serum albumin.

Metabolism

Norgestimate is extensively metabolized by first-pass mechanisms in the gastrointestinal tract and/or liver. Norgestimate's primary active metabolite is norelgestromin. Subsequent hepatic metabolism of norelgestromin occurs and metabolites include norgestrel, which is also active and various hydroxylated and conjugated metabolites. Ethinyl estradiol is also metabolized to various hydroxylated products and their glucuronide and sulfate conjugates.

Excretion

Following 3 cycles of administration of ORTHO TRI-CYCLEN® Lo, the mean (± SD) elimination half-life values, at steady-state, for norelgestromin, norgestrel and ethinyl estradiol were 28.1 (± 10.6) hours, 36.4 (± 10.2) hours and 17.7 (± 4.4) hours, respectively (Table 1). The metabolites of norelgestromin and ethinyl estradiol are eliminated by renal and fecal pathways.

Special Populations

Effects of Body Weight, Body Surface Area, and Age

The effects of body weight, body surface area, age and race on the pharmacokinetics of norelgestromin, norgestrel and ethinyl estradiol were evaluated in 79 healthy women using pooled data following single dose administration of NGM 180 or 250 mcg / EE 25 mcg tablets in four pharmacokinetic studies. Increasing body weight and body surface area were each associated with decreases in Cmax and AUC0–24h values for norelgestromin and ethinyl estradiol and increases in CL/F (oral clearance) for ethinyl estradiol. Increasing body weight by 10 kg is predicted to reduce the following parameters: NGMN Cmax by 9% and AUC0–24h by 19%, norgestrel Cmax by 12% and AUC0–24h by 46%, EE Cmax by 13% and AUC0–24h by 12%. These changes were statistically significant. Increasing age was associated with slight decreases (6% with increasing age by 5 years) in Cmax and AUC0–24h for norelgestromin and were statistically significant, but there was no significant effect for norgestrel or ethinyl estradiol. Only a small to moderate fraction (5–40%) of the overall variability in the pharmacokinetics of norelgestromin and ethinyl estradiol following ORTHO TRI-CYCLEN® Lo Tablets may be explained by any or all of the above demographic parameters.

In clinical studies involving 1673 subjects with a mean weight of 141 pounds, there was no association between pregnancy and weight.

Renal and Hepatic Impairment

No studies with ORTHO TRI-CYCLEN® Lo have been conducted in women with renal or hepatic impairment.

Drug-Drug Interactions

Although norelgestromin and its metabolites inhibit a variety of P450 enzymes in human liver microsomes, under the recommended dosing regimen, the in vivo concentrations of norelgestromin and its metabolites, even at the peak serum levels, are relatively low compared to the inhibitory constant (Ki).

Interactions between oral contraceptives and other drugs have been reported in the literature. No formal drug-drug interaction studies were conducted with ORTHO TRI-CYCLEN® Lo (see PRECAUTIONS).

INDICATIONS AND USAGE

ORTHO TRI-CYCLEN® Lo Tablets are indicated for the prevention of pregnancy in women who elect to use oral contraceptives as a method of contraception.

In an active controlled clinical trial 1,673 subjects completed 11,003 cycles of ORTHO TRI-CYCLEN® Lo use and a total of 20 pregnancies were reported in ORTHO TRI-CYCLEN® Lo users.^99 This represents an overall use-efficacy (typical user efficacy) pregnancy rate of 2.36 per 100 women-years of use.

Oral contraceptives are highly effective for pregnancy prevention. Table 2 lists the typical accidental pregnancy rates for users of combination oral contraceptives and other methods of contraception. The efficacy of these contraceptive methods, except sterilization, the IUD, and the Norplant® system, depends upon the reliability with which they are used. Correct and consistent use of methods can result in lower failure rates.

Table 2: Percentage of Women Experiencing an Unintended Pregnancy During the First Year of Typical Use and the First Year of Perfect Use of Contraception and the Percentage Continuing Use at the End of the First Year. United States.
 | % of Women Experiencing an Unintended Pregnancy Within the First Year of Use |  | % of Women Continuing Use at One Year
Method | Typical Use | Perfect Use
(1) | (2) | (3) | (4)
Chance | 85 | 85
Spermicides | 26 | 6 | 40
Periodic abstinence | 25 |  | 63
Calendar |  | 9
Ovulation Method |  | 3
Sympto-Thermal |  | 2
Post-Ovulation |  | 1
Withdrawal | 19 | 4
Cap [With spermicidal cream or jelly.]
Parous Women | 40 | 26 | 42
Nulliparous Women | 20 | 9 | 56
Sponge
Parous Women | 40 | 20 | 42
Nulliparous Women | 20 | 9 | 56
Diaphragm | 20 | 6 | 56
Condom
Female (Reality®) | 21 | 5 | 56
Male | 14 | 3 | 61
Pill | 5 |  | 71
Progestin Only |  | 0.5
Combined |  | 0.1
IUD
Progesterone T | 2.0 | 1.5 | 81
Copper T380A | 0.8 | 0.6 | 78
LNg 20 | 0.1 | 0.1 | 81
Depo-Provera® | 0.3 | 0.3 | 70
Norplant® and Norplant-2® | 0.05 | 0.05 | 88
Female Sterilization | 0.5 | 0.5 | 100
Male Sterilization | 0.15 | 0.10 | 100
Emergency Contraceptive Pills: Treatment initiated within 72 hours after unprotected intercourse reduces the risk of pregnancy by at least 75%. [The treatment schedule is one dose within 72 hours after unprotected intercourse, and a second dose 12 hours after the first dose. The FDA has declared the following brands of oral contraceptives to be safe and effective for emergency contraception: Ovral® (1 dose is 2 white pills), Alesse® (1 dose is 5 pink pills), Nordette® or Levlen® (1 dose is 4 yellow pills).]
Lactation Amenorrhea Method: LAM is a highly effective, temporary method of contraception. [However, to maintain effective protection against pregnancy, another method of contraception must be used as soon as menstruation resumes, the frequency or duration of breastfeeds is reduced, bottle feeds are introduced, or the baby reaches 6 months of age.]
Source: Trussell J. Contraceptive efficacy. In Hatcher RA, Trussell J, Stewart F, Cates W, Stewart GK, Kowel D, Guest F, Contraceptive Technology: Seventeenth Revised Edition. New York NY: Irvington Publishers, 1998.

ORTHO TRI-CYCLEN® Lo has not been studied for and is not indicated for use in emergency contraception.

CONTRAINDICATIONS

Oral contraceptives should not be used in women who have any of the following conditions:

- Thrombophlebitis or thromboembolic disorders
- A past history of deep vein thrombophlebitis or thromboembolic disorders
- Cerebral vascular or coronary artery disease (current or history)
- Valvular heart disease with complications
- Severe hypertension
- Diabetes with vascular involvement
- Headaches with focal neurological symptoms
- Major surgery with prolonged immobilization
- Known or suspected carcinoma of the breast or personal history of breast cancer
- Carcinoma of the endometrium or other known or suspected estrogen-dependent neoplasia
- Undiagnosed abnormal genital bleeding
- Cholestatic jaundice of pregnancy or jaundice with prior pill use
- Hepatic adenomas or carcinomas
- Known or suspected pregnancy
- Hypersensitivity to any component of this product

WARNINGS

BOXED WARNING

Cigarette smoking increases the risk of serious cardiovascular side effects from oral contraceptive use. This risk increases with age and with heavy smoking (15 or more cigarettes per day) and is quite marked in women over 35 years of age. Women who use oral contraceptives should be strongly advised not to smoke.

The use of oral contraceptives is associated with increased risks of several serious conditions including myocardial infarction, thromboembolism, stroke, hepatic neoplasia, and gallbladder disease, although the risk of serious morbidity or mortality is very small in healthy women without underlying risk factors. The risk of morbidity and mortality increases significantly in the presence of other underlying risk factors such as hypertension, hyperlipidemias, obesity and diabetes.

Practitioners prescribing oral contraceptives should be familiar with the following information relating to these risks.

The information contained in this package insert is principally based on studies carried out in patients who used oral contraceptives with higher formulations of estrogens and progestogens than those in common use today. The effect of long-term use of the oral contraceptives with lower formulations of both estrogens and progestogens remains to be determined.

Throughout this labeling, epidemiological studies reported are of two types: retrospective or case control studies and prospective or cohort studies. Case control studies provide a measure of the relative risk of a disease, namely, a ratio of the incidence of a disease among oral contraceptive users to that among nonusers. The relative risk does not provide information on the actual clinical occurrence of a disease. Cohort studies provide a measure of attributable risk, which is the difference in the incidence of disease between oral contraceptive users and nonusers. The attributable risk does provide information about the actual occurrence of a disease in the population (adapted from refs. 2 and 3 with the author's permission). For further information, the reader is referred to a text on epidemiological methods.

1. Thromboembolic Disorders and Other Vascular Problems

a. Myocardial Infarction

An increased risk of myocardial infarction has been attributed to oral contraceptive use. This risk is primarily in smokers or women with other underlying risk factors for coronary artery disease such as hypertension, hypercholesterolemia, morbid obesity, and diabetes. The relative risk of heart attack for current oral contraceptive users has been estimated to be two to six.^4–10 The risk is very low under the age of 30.

Smoking in combination with oral contraceptive use has been shown to contribute substantially to the incidence of myocardial infarctions in women in their mid-thirties or older with smoking accounting for the majority of excess cases.^11 Mortality rates associated with circulatory disease have been shown to increase substantially in smokers, especially in those 35 years of age and older and in nonsmokers over the age of 40 among women who use oral contraceptives.

Figure 1: Circulatory Disease Mortality Rates per 100,000 Women-Years by Age, Smoking Status and Oral Contraceptive Use

Figure 1 Adapted from P.M. Layde and V. Beral, Ref. #12.

Oral contraceptives may compound the effects of well-known risk factors, such as hypertension, diabetes, hyperlipidemias, age and obesity.^13 In particular, some progestogens are known to decrease HDL cholesterol and cause glucose intolerance, while estrogens may create a state of hyperinsulinism.^14–18 Oral contraceptives have been shown to increase blood pressure among users (see section 9 in WARNINGS). Similar effects on risk factors have been associated with an increased risk of heart disease. Oral contraceptives must be used with caution in women with cardiovascular disease risk factors.

Norgestimate has minimal androgenic activity (see CLINICAL PHARMACOLOGY), and there is some evidence that the risk of myocardial infarction associated with oral contraceptives is lower when the progestogen has minimal androgenic activity than when the activity is greater.^97

b. Thromboembolism

An increased risk of thromboembolic and thrombotic disease associated with the use of oral contraceptives is well established. Case control studies have found the relative risk of users compared to nonusers to be 3 for the first episode of superficial venous thrombosis, 4 to 11 for deep vein thrombosis or pulmonary embolism, and 1.5 to 6 for women with predisposing conditions for venous thromboembolic disease.^2,3,19–24 Cohort studies have shown the relative risk to be somewhat lower, about 3 for new cases and about 4.5 for new cases requiring hospitalization.^25 The risk of thromboembolic disease associated with oral contraceptives is not related to length of use and disappears after pill use is stopped.^2

A two- to four-fold increase in relative risk of post-operative thromboembolic complications has been reported with the use of oral contraceptives.^9 The relative risk of venous thrombosis in women who have predisposing conditions is twice that of women without such medical conditions.^26 If feasible, oral contraceptives should be discontinued at least four weeks prior to and for two weeks after elective surgery of a type associated with an increase in risk of thromboembolism and during and following prolonged immobilization. Since the immediate postpartum period is also associated with an increased risk of thromboembolism, oral contraceptives should be started no earlier than four weeks after delivery in women who elect not to breastfeed.

c. Cerebrovascular Diseases

Oral contraceptives have been shown to increase both the relative and attributable risks of cerebrovascular events (thrombotic and hemorrhagic strokes), although, in general, the risk is greatest among older (>35 years), hypertensive women who also smoke. Hypertension was found to be a risk factor for both users and nonusers, for both types of strokes, and smoking interacted to increase the risk of hemorrhagic stroke.^27–29

In a large study, the relative risk of thrombotic strokes has been shown to range from 3 for normotensive users to 14 for users with severe hypertension.^30 The relative risk of hemorrhagic stroke is reported to be 1.2 for non-smokers who used oral contraceptives, 2.6 for smokers who did not use oral contraceptives, 7.6 for smokers who used oral contraceptives, 1.8 for normotensive users and 25.7 for users with severe hypertension.^30 The attributable risk is also greater in older women.^3

d. Dose-Related Risk of Vascular Disease from Oral Contraceptives

A positive association has been observed between the amount of estrogen and progestogen in oral contraceptives and the risk of vascular disease.^31–33 A decline in serum high density lipoproteins (HDL) has been reported with many progestational agents.^14–16 A decline in serum high density lipoproteins has been associated with an increased incidence of ischemic heart disease. Because estrogens increase HDL cholesterol, the net effect of an oral contraceptive depends on a balance achieved between doses of estrogen and progestogen and the activity of the progestogen used in the contraceptives. The activity and amount of both hormones should be considered in the choice of an oral contraceptive.

Minimizing exposure to estrogen and progestogen is in keeping with good principles of therapeutics. For any particular estrogen/progestogen combination, the dosage regimen prescribed should be one which contains the least amount of estrogen and progestogen that is compatible with a low failure rate and the needs of the individual patient. New acceptors of oral contraceptive agents should be started on preparations containing the lowest estrogen content which is judged appropriate for an individual patient.

e. Persistence of Risk of Vascular Disease

There are two studies which have shown persistence of risk of vascular disease for ever-users of oral contraceptives. In a study in the United States, the risk of developing myocardial infarction after discontinuing oral contraceptives persists for at least 9 years for women 40–49 years who had used oral contraceptives for five or more years, but this increased risk was not demonstrated in other age groups.^8 In another study in Great Britain, the risk of developing cerebrovascular disease persisted for at least 6 years after discontinuation of oral contraceptives, although excess risk was very small.^34 However, both studies were performed with oral contraceptive formulations containing 50 micrograms or higher of estrogens.

2. Estimates of Mortality from Contraceptive Use

One study gathered data from a variety of sources which have estimated the mortality rate associated with different methods of contraception at different ages (Table 3). These estimates include the combined risk of death associated with contraceptive methods plus the risk attributable to pregnancy in the event of method failure. Each method of contraception has its specific benefits and risks. The study concluded that with the exception of oral contraceptive users 35 and older who smoke, and 40 and older who do not smoke, mortality associated with all methods of birth control is low and below that associated with childbirth. The observation of an increase in risk of mortality with age for oral contraceptive users is based on data gathered in the 1970's.^35 Current clinical recommendation involves the use of lower estrogen dose formulations and a careful consideration of risk factors. In 1989, the Fertility and Maternal Health Drugs Advisory Committee was asked to review the use of oral contraceptives in women 40 years of age and over.

The Committee concluded that although cardiovascular disease risks may be increased with oral contraceptive use after age 40 in healthy non-smoking women (even with the newer low-dose formulations), there are also greater potential health risks associated with pregnancy in older women and with the alternative surgical and medical procedures which may be necessary if such women do not have access to effective and acceptable means of contraception. The Committee recommended that the benefits of low-dose oral contraceptive use by healthy non-smoking women over 40 may outweigh the possible risks.

Of course, older women, as all women, who take oral contraceptives, should take an oral contraceptive which contains the least amount of estrogen and progestogen that is compatible with a low failure rate and individual patient needs.

Table 3: Annual Number of Birth-Related or Method-Related Deaths Associated with Control of Fertility per 100,000 Nonsterile Women, by Fertility-Control Method and According to Age
Method of control and outcome | 15–19 | 20–24 | 25–29 | 30–34 | 35–39 | 40–44
No fertility-control methods [Deaths are birth-related] | 7.0 | 7.4 | 9.1 | 14.8 | 25.7 | 28.2
Oral contraceptives, non-smoker [Deaths are method-related] | 0.3 | 0.5 | 0.9 | 1.9 | 13.8 | 31.6
Oral contraceptives, smoker | 2.2 | 3.4 | 6.6 | 13.5 | 51.1 | 117.2
IUD | 0.8 | 0.8 | 1.0 | 1.0 | 1.4 | 1.4
Condom | 1.1 | 1.6 | 0.7 | 0.2 | 0.3 | 0.4
Diaphragm/spermicide | 1.9 | 1.2 | 1.2 | 1.3 | 2.2 | 2.8
Periodic abstinence | 2.5 | 1.6 | 1.6 | 1.7 | 2.9 | 3.6
Adapted from H.W. Ory, Family Planning Perspectives, Ref. #35.

3. Carcinoma of the Reproductive Organs and Breasts

Numerous epidemiological studies have been performed on the incidence of breast, endometrial, ovarian, and cervical cancer in women using oral contraceptives.

The risk of having breast cancer diagnosed may be slightly increased among current and recent users of combination oral contraceptives. However, this excess risk appears to decrease over time after discontinuation of combination oral contraceptives and by 10 years after cessation the increased risk disappears. Some studies report an increased risk with duration of use while other studies do not and no consistent relationships have been found with dose or type of steroid. Some studies have found a small increase in risk for women who first use combination oral contraceptives before age 20. Most studies show a similar pattern of risk with combination oral contraceptive use regardless of a woman's reproductive history or her family breast cancer history.

Breast cancers diagnosed in current or previous oral contraceptive users tend to be less clinically advanced than in nonusers.

Women who currently have or have had breast cancer should not use oral contraceptives because breast cancer is usually a hormonally-sensitive tumor.

Some studies suggest that oral contraceptive use has been associated with an increase in the risk of cervical intraepithelial neoplasia in some populations of women.^45–48 However, there continues to be controversy about the extent to which such findings may be due to differences in sexual behavior and other factors.

In spite of many studies of the relationship between oral contraceptive use and breast and cervical cancers, a cause-and-effect relationship has not been established.

4. Hepatic Neoplasia

Benign hepatic adenomas are associated with oral contraceptive use, although the incidence of benign tumors is rare in the United States. Indirect calculations have estimated the attributable risk to be in the range of 3.3 cases/100,000 for users, a risk that increases after four or more years of use especially with oral contraceptives of higher dose.^49 Rupture of benign, hepatic adenomas may cause death through intra-abdominal hemorrhage.^50,51

Studies from Britain have shown an increased risk of developing hepatocellular carcinoma in long-term (>8 years) oral contraceptive users. However, these cancers are extremely rare in the U.S. and the attributable risk (the excess incidence) of liver cancers in oral contraceptive users approaches less than one per million users.

5. Ocular Lesions

There have been clinical case reports of retinal thrombosis associated with the use of oral contraceptives. Oral contraceptives should be discontinued if there is unexplained partial or complete loss of vision; onset of proptosis or diplopia; papilledema; or retinal vascular lesions. Appropriate diagnostic and therapeutic measures should be undertaken immediately.

6. Oral Contraceptive Use Before or During Early Pregnancy

Extensive epidemiological studies have revealed no increased risk of birth defects in women who have used oral contraceptives prior to pregnancy.^56,57 The majority of recent studies also do not indicate a teratogenic effect, particularly in so far as cardiac anomalies and limb reduction defects are concerned,^55,56,58,59 when taken inadvertently during early pregnancy.

The administration of oral contraceptives to induce withdrawal bleeding should not be used as a test for pregnancy. Oral contraceptives should not be used during pregnancy to treat threatened or habitual abortion.

It is recommended that for any patient who has missed two consecutive periods, pregnancy should be ruled out. If the patient has not adhered to the prescribed schedule, the possibility of pregnancy should be considered at the time of the first missed period. Oral contraceptive use should be discontinued if pregnancy is confirmed.

7. Gallbladder Disease

Earlier studies have reported an increased lifetime relative risk of gallbladder surgery in users of oral contraceptives and estrogens.^60,61 More recent studies, however, have shown that the relative risk of developing gallbladder disease among oral contraceptive users may be minimal.^62–64 The recent findings of minimal risk may be related to the use of oral contraceptive formulations containing lower hormonal doses of estrogens and progestogens.

8. Carbohydrate and Lipid Metabolic Effects

Oral contraceptives have been shown to cause a decrease in glucose tolerance in a significant percentage of users.^17 This effect has been shown to be directly related to estrogen dose.^65 Progestogens increase insulin secretion and create insulin resistance, this effect varying with different progestational agents.^17,66 However, in the non-diabetic woman, oral contraceptives appear to have no effect on fasting blood glucose.^67 Because of these demonstrated effects, prediabetic and diabetic women in particular should be carefully monitored while taking oral contraceptives.

A small proportion of women will have persistent hypertriglyceridemia while on the pill. As discussed earlier (see WARNINGS 1a and 1d), changes in serum triglycerides and lipoprotein levels have been reported in oral contraceptive users.

9. Elevated Blood Pressure

Women with significant hypertension should not be started on hormonal contraception.^98 An increase in blood pressure has been reported in women taking oral contraceptives^68 and this increase is more likely in older oral contraceptive users^69 and with extended duration of use.^61 Data from the Royal College of General Practitioners^12 and subsequent randomized trials have shown that the incidence of hypertension increases with increasing progestational activity and concentrations of progestogens.

Women with a history of hypertension or hypertension-related diseases, or renal disease^70 should be encouraged to use another method of contraception. If women elect to use oral contraceptives, they should be monitored closely and if significant elevation of blood pressure occurs, oral contraceptives should be discontinued. For most women, elevated blood pressure will return to normal after stopping oral contraceptives, and there is no difference in the occurrence of hypertension between former and never users.^68–71

10. Headache

The onset or exacerbation of migraine or development of headache with a new pattern which is recurrent, persistent or severe requires discontinuation of oral contraceptives and evaluation of the cause.

11. Bleeding Irregularities

Breakthrough bleeding and spotting are sometimes encountered in patients on oral contraceptives, especially during the first three months of use. Non-hormonal causes should be considered and adequate diagnostic measures taken to rule out malignancy or pregnancy in the event of breakthrough bleeding, as in the case of any abnormal vaginal bleeding. If pathology has been excluded, time or a change to another formulation may solve the problem. In the event of amenorrhea, pregnancy should be ruled out.

Some women may encounter post-pill amenorrhea or oligomenorrhea, especially when such a condition was preexistent.

12. Ectopic Pregnancy

Ectopic as well as intrauterine pregnancy may occur in contraceptive failures.

PRECAUTIONS

1. General

Patients should be counseled that this product does not protect against HIV infection (AIDS) and other sexually transmitted diseases.

2. Physical Examination and Follow-Up

It is good medical practice for all women to have annual history and physical examinations, including women using oral contraceptives. The physical examination, however, may be deferred until after initiation of oral contraceptives if requested by the woman and judged appropriate by the clinician. The physical examination should include special reference to blood pressure, breasts, abdomen and pelvic organs, including cervical cytology, and relevant laboratory tests. In case of undiagnosed, persistent or recurrent abnormal vaginal bleeding, appropriate measures should be conducted to rule out malignancy. Women with a strong family history of breast cancer or who have breast nodules should be monitored with particular care.

3. Lipid Disorders

Women who are being treated for hyperlipidemias should be followed closely if they elect to use oral contraceptives. Some progestogens may elevate LDL levels and may render the control of hyperlipidemias more difficult.

4. Liver Function

If jaundice develops in any woman receiving oral contraceptives, the medication should be discontinued. Steroid hormones may be poorly metabolized in patients with impaired liver function.

5. Fluid Retention

Oral contraceptives may cause some degree of fluid retention. They should be prescribed with caution, and only with careful monitoring, in patients with conditions which might be aggravated by fluid retention.

6. Emotional Disorders

Women with a history of depression should be carefully observed and the drug discontinued if depression recurs to a serious degree.

7. Contact Lenses

Contact lens wearers who develop visual changes or changes in lens tolerance should be assessed by an ophthalmologist.

8. Drug Interactions

Changes in contraceptive effectiveness associated with co-administration of other products

Contraceptive effectiveness may be reduced when hormonal contraceptives are coadministered with antibiotics, anticonvulsants, and other drugs that increase the metabolism of contraceptive steroids. This could result in unintended pregnancy or breakthrough bleeding. Examples include rifampin, barbiturates, phenylbutazone, phenytoin, carbamazepine, felbamate, oxcarbazepine, topiramate, griseofulvin and bosentan. Several cases of contraceptive failure and breakthrough bleeding have been reported in the literature with concomitant administration of antibiotics such as ampicillin and tetracyclines. However, clinical pharmacology studies investigating drug interaction between combined oral contraceptives and these antibiotics have reported inconsistent results.

Several of the anti-HIV protease inhibitors have been studied with co-administration of oral combination hormonal contraceptives; significant changes (increase and decrease) in the plasma levels of the estrogen and progestin have been noted in some cases. The safety and efficacy of oral contraceptive products may be affected with coadministration of anti-HIV protease inhibitors. Healthcare professionals should refer to the label of the individual anti-HIV protease inhibitors for further drug-drug interaction information.

Herbal products containing St. John's Wort (hypericum perforatum) may induce hepatic enzymes (cytochrome P450) and p-glycoprotein transporter and may reduce the effectiveness of contraceptive steroids. This may also result in breakthrough bleeding.

Concurrent use of bosentan and ethinyl estradiol containing products may result in decreased concentrations of these contraceptive hormones thereby increasing the risk of unintended pregnancy and unscheduled bleeding.

Increase in plasma ethinyl estradiol levels associated with co-administered drugs

Co-administration of atorvastatin and certain oral contraceptives containing ethinyl estradiol increase AUC values for ethinyl estradiol by approximately 20%. Ascorbic acid and acetaminophen may increase plasma ethinyl estradiol levels, possibly by inhibition of conjugation. CYP 3A4 inhibitors such as itraconazole or ketoconazole may increase plasma hormone levels.

Changes in plasma levels of co-administered drugs

Combination hormonal contraceptives containing some synthetic estrogens (e.g., ethinyl estradiol) may inhibit the metabolism of other compounds. Increased plasma concentrations of cyclosporin, prednisolone, and theophylline have been reported with concomitant administration of oral contraceptives. Decreased plasma concentrations of acetaminophen and increased clearance of temazepam, salicylic acid, morphine and clofibric acid, due to induction of conjugation, have been noted when drugs were administered with oral contraceptives.

Combined hormonal contraceptives have been shown to significantly decrease plasma concentrations of lamotrigine when co-administered due to induction of lamotrigine glucuronidation. This may reduce seizure control; therefore, dosage adjustments of lamotrigine may be necessary.^103

Healthcare professionals are advised to also refer to prescribing information of co-administered drugs for recommendations regarding management of concomitant therapy.

9. Interactions with Laboratory Tests

Certain endocrine and liver function tests and blood components may be affected by oral contraceptives:

1. Increased prothrombin and factors VII, VIII, IX, and X; decreased antithrombin 3; increased norepinephrine-induced platelet aggregability.
2. Increased thyroid binding globulin (TBG) leading to increased circulating total thyroid hormone, as measured by protein-bound iodine (PBI), T4 by column or by radioimmunoassay. Free T3 resin uptake is decreased, reflecting the elevated TBG, free T4 concentration is unaltered.
3. Other binding proteins may be elevated in serum.
4. Sex hormone binding globulins are increased and result in elevated levels of total circulating sex steroids; however, free or biologically active levels either decrease or remain unchanged.
5. Triglycerides may be increased and levels of various other lipids and lipoproteins may be affected.
6. Glucose tolerance may be decreased.
7. Serum folate levels may be depressed by oral contraceptive therapy. This may be of clinical significance if a woman becomes pregnant shortly after discontinuing oral contraceptives.

10. Carcinogenesis

See WARNINGS.

11. Pregnancy

Pregnancy Category X

See CONTRAINDICATIONS and WARNINGS.

12. Nursing Mothers

Small amounts of oral contraceptive steroids have been identified in the milk of nursing mothers and a few adverse effects on the child have been reported, including jaundice and breast enlargement. In addition, oral contraceptives given in the postpartum period may interfere with lactation by decreasing the quantity and quality of breast milk. If possible, the nursing mother should be advised not to use combination oral contraceptives but to use other forms of contraception until she has completely weaned her child.

13. Pediatric Use

Safety and efficacy of ORTHO TRI-CYCLEN® Lo Tablets have been established in women of reproductive age. Safety and efficacy are expected to be the same for postpubertal adolescents under the age of 16 and for users 16 years and older. Use of this product before menarche is not indicated.

14. Geriatric Use

This product has not been studied in women over 65 years of age and is not indicated in this population.

INFORMATION FOR THE PATIENT

See Patient Labeling printed below.

ADVERSE REACTIONS

An increased risk of the following serious adverse reactions has been associated with the use of oral contraceptives (see WARNINGS).

- Thrombophlebitis and venous thrombosis with or without embolism
- Arterial thromboembolism
- Pulmonary embolism
- Myocardial infarction
- Cerebral hemorrhage
- Cerebral thrombosis
- Hypertension
- Gallbladder disease
- Hepatic adenomas or benign liver tumors

There is evidence of an association between the following conditions and the use of oral contraceptives:

- Mesenteric thrombosis
- Retinal thrombosis

The following adverse reactions have been reported in patients receiving oral contraceptives and are believed to be drug-related:

- Nausea
- Vomiting
- Gastrointestinal symptoms (such as abdominal cramps and bloating)
- Breakthrough bleeding
- Spotting
- Change in menstrual flow
- Amenorrhea
- Temporary infertility after discontinuation of treatment
- Edema
- Melasma which may persist
- Breast changes: tenderness, enlargement, secretion
- Change in weight (increase or decrease)
- Change in cervical erosion and secretion
- Diminution in lactation when given immediately postpartum
- Cholestatic jaundice
- Migraine
- Allergic reaction, including rash, urticaria, and angioedema
- Mental depression
- Reduced tolerance to carbohydrates
- Vaginal candidiasis
- Change in corneal curvature (steepening)
- Intolerance to contact lenses

The following adverse reactions have been reported in users of oral contraceptives and the association has been neither confirmed nor refuted:

- Pre-menstrual syndrome
- Cataracts
- Changes in appetite
- Cystitis-like syndrome
- Headache
- Nervousness
- Dizziness
- Hirsutism
- Loss of scalp hair
- Erythema multiforme
- Erythema nodosum
- Hemorrhagic eruption
- Vaginitis
- Porphyria
- Impaired renal function
- Hemolytic uremic syndrome
- Acne
- Changes in libido
- Colitis
- Budd-Chiari Syndrome

OVERDOSAGE

Serious ill effects have not been reported following acute ingestion of large doses of oral contraceptives by young children. Overdosage may cause nausea and withdrawal bleeding may occur in females.

NON-CONTRACEPTIVE HEALTH BENEFITS

The following non-contraceptive health benefits related to the use of combination oral contraceptives are supported by epidemiological studies which largely utilized oral contraceptive formulations containing estrogen doses exceeding 0.035 mg of ethinyl estradiol or 0.05 mg mestranol.^73–78

Effects on menses:

- increased menstrual cycle regularity
- decreased blood loss and decreased incidence of iron deficiency anemia
- decreased incidence of dysmenorrhea

Effects related to inhibition of ovulation:

- decreased incidence of functional ovarian cysts
- decreased incidence of ectopic pregnancies

Other effects:

- decreased incidence of fibroadenomas and fibrocystic disease of the breast
- decreased incidence of acute pelvic inflammatory disease
- decreased incidence of endometrial cancer
- decreased incidence of ovarian cancer

DOSAGE AND ADMINISTRATION

Oral Contraception

To achieve maximum contraceptive effectiveness, ORTHO TRI-CYCLEN® Lo Tablets must be taken exactly as directed and at intervals not exceeding 24 hours. The possibility of ovulation and conception prior to initiation of medication should be considered. ORTHO TRI-CYCLEN® Lo is available with the DIALPAK® Tablet Dispenser which is preset for a Sunday Start. Day 1 Start is also provided.

Sunday Start

When taking ORTHO TRI-CYCLEN® Lo the first white "active" tablet should be taken on the first Sunday after menstruation begins. If the menstrual period begins on Sunday, the first white "active" tablet should be taken that day. Take one white, light blue or dark blue "active" tablet daily for 21 days followed by one dark green "reminder" tablet daily for 7 days. After 28 tablets have been taken, a new course is started the next day (Sunday). For the first cycle of a Sunday Start regimen, another method of contraception should be used until after the first 7 consecutive days of administration.

If the patient misses one (1) white, light blue, or dark blue "active" tablet in Weeks 1, 2, or 3, the tablet should be taken as soon as she remembers. If the patient misses two (2) white or light blue "active" tablets in Week 1 or Week 2, the patient should take two (2) "active" tablets the day she remembers and two (2) "active" tablets the next day; and then continue taking one (1) tablet a day until she finishes the pack. The patient should be instructed to use a back-up method of birth control if she has sex in the seven (7) days after missing pills. If the patient misses two (2) dark blue "active" tablets in the third week or misses three (3) or more "active" tablets in a row, the patient should continue taking one tablet every day until Sunday. On Sunday the patient should throw out the rest of the pack and start a new pack that same day. The patient should be instructed to use a back-up method of birth control if she has sex in the seven (7) days after missing pills.

Complete instructions to facilitate patient counseling on proper pill usage may be found in the Detailed Patient Labeling ("How to Take the Pill" section).

Day 1 Start

The dosage of ORTHO TRI-CYCLEN® Lo for the initial cycle of therapy is one white, light blue or dark blue "active" tablet administered daily from the 1st day through the 21st day of the menstrual cycle, counting the first day of menstrual flow as "Day 1" followed by one dark green "reminder" tablet daily for 7 days. Tablets are taken without interruption for 28 days. After 28 tablets have been taken, a new course is started the next day.

If the patient misses one (1) white, light blue, or dark blue "active" tablet in Weeks 1, 2, or 3, the tablet should be taken as soon as she remembers. If the patient misses two (2) white or light blue "active" tablets in Week 1 or Week 2, the patient should take two (2) "active" tablets the day she remembers and two (2) "active" tablets the next day; and then continue taking one (1) tablet a day until she finishes the pack. The patient should be instructed to use a back-up method of birth control if she has sex in the seven (7) days after missing pills. If the patient misses two (2) dark blue "active" tablets in the third week or misses three (3) or more "active" tablets in a row, the patient should throw out the rest of the pack and start a new pack that same day. The patient should be instructed to use a back-up method of birth control if she has sex in the seven (7) days after missing pills.

Complete instructions to facilitate patient counseling on proper pill usage may be found in the Detailed Patient Labeling ("How to Take the Pill" section).

When switching from another oral contraceptive, ORTHO TRI-CYCLEN® Lo should be started on the same day that a new pack of the previous oral contraceptive would have been started.

The use of ORTHO TRI-CYCLEN® Lo for contraception may be initiated 4 weeks postpartum in women who elect not to breastfeed. When the tablets are administered during the postpartum period, the increased risk of thromboembolic disease associated with the postpartum period must be considered. (See CONTRAINDICATIONS and WARNINGS concerning thromboembolic disease. See also PRECAUTIONS: Nursing Mothers.) The possibility of ovulation and conception prior to initiation of medication should be considered.

(See Discussion of Dose-Related Risk of Vascular Disease from Oral Contraceptives.)

ADDITIONAL INSTRUCTIONS FOR ALL DOSING REGIMENS

Breakthrough bleeding, spotting, and amenorrhea are frequent reasons for patients discontinuing oral contraceptives. In breakthrough bleeding, as in all cases of irregular bleeding from the vagina, nonfunctional causes should be borne in mind. In undiagnosed persistent or recurrent abnormal bleeding from the vagina, adequate diagnostic measures are indicated to rule out pregnancy or malignancy. If pathology has been excluded, time or a change to another formulation may solve the problem. Changing to an oral contraceptive with a higher estrogen content, while potentially useful in minimizing menstrual irregularity, should be done only if necessary since this may increase the risk of thromboembolic disease.

Use of oral contraceptives in the event of a missed menstrual period:

1. If the patient has not adhered to the prescribed schedule, the possibility of pregnancy should be considered at the time of the first missed period and oral contraceptive use should be discontinued if pregnancy is confirmed.
2. If the patient has adhered to the prescribed regimen and misses two consecutive periods, pregnancy should be ruled out before continuing oral contraceptive use.

HOW SUPPLIED

ORTHO TRI-CYCLEN® Lo Tablets are available in a blister card (NDC 54868-4730-0) with a DIALPAK® Tablet Dispenser (unfilled). The blister card contains 28 tablets. Each of the 7 white, round, convex, coated tablets imprinted "O-M" on one side and "180" on the other side contains 0.180 mg of the progestational compound, norgestimate, together with 0.025 mg of the estrogenic compound, ethinyl estradiol. Each of the 7 light blue, round, convex, coated tablets imprinted "O-M" on one side and "215" on the other side contains 0.215 mg of the progestational compound, norgestimate, together with 0.025 mg of the estrogenic compound, ethinyl estradiol. Each of the 7 dark blue, round, convex, coated tablets imprinted "O-M" on one side and "250" on the other side contains 0.250 mg of the progestational compound, norgestimate, together with 0.025 mg of the estrogenic compound, ethinyl estradiol. Each of the 7 dark green, round, convex, coated tablets imprinted "O-M" on one side and "P" on the other side contains inert ingredients.

STORAGE AND HANDLING

Store at 25°C (77°F); excursions permitted to 15° – 30°C (59° – 86°F).

Protect from light.

REFERENCES

1. Trussell J. Contraceptive efficacy. In Hatcher RA, Trussell J, Stewart F, Cates W, Stewart GK, Kowal D, Guest F, Contraceptive Technology: Seventeenth Revised Edition. New York NY: Irvington Publishers, 1998.
2. Stadel BV, Oral contraceptives and cardiovascular disease. (Pt.1). N Engl J Med 1981; 305:612–618.
3. Stadel BV, Oral contraceptives and cardiovascular disease. (Pt.2). N Engl J Med 1981; 305:672–677.
4. Adam SA, Thorogood M. Oral contraception and myocardial infarction revisited: the effects of new preparations and prescribing patterns. Br J Obstet Gynaecol 1981; 88:838–845.
5. Mann JI, Inman WH. Oral contraceptives and death from myocardial infarction. Br Med J 1975; 2(5965):245–248.
6. Mann JI, Vessey MP, Thorogood M, Doll R. Myocardial infarction in young women with special reference to oral contraceptive practice. Br Med J 1975; 2(5956):241–245.
7. Royal College of General Practitioners' Oral Contraception Study: Further analyses of mortality in oral contraceptive users. Lancet 1981; 1:541–546.
8. Slone D, Shapiro S, Kaufman DW, Rosenberg L, Miettinen OS, Stolley PD. Risk of myocardial infarction in relation to current and discontinued use of oral contraceptives. N Engl J Med 1981:305:420–424.
9. Vessey MP. Female hormones and vascular disease - an epidemiological overview. Br J Fam Plann 1980; 6(Supplement): 1–12.
10. Russell-Briefel RG, Ezzati TM, Fulwood R, Perlman JA, Murphy RS. Cardiovascular risk status and oral contraceptive use, United States, 1976–80. Prevent Med 1986; 15:352–362.
11. Goldbaum GM, Kendrick JS, Hogelin GC, Gentry EM. The relative impact of smoking and oral contraceptive use on women in the United States. JAMA 1987; 258:1339–1342.
12. Layde PM, Beral V. Further analyses of mortality in oral contraceptive users; Royal College of General Practitioners' Oral Contraception Study. (Table 5) Lancet 1981; 1:541–546.
13. Knopp RH. Arteriosclerosis risk: the roles of oral contraceptives and postmenopausal estrogens. J Reprod Med 1986; 31(9) (Supplement):913–921.
14. Krauss RM, Roy S, Mishell DR, Casagrande J, Pike MC. Effects of two low-dose oral contraceptives on serum lipids and lipoproteins: Differential changes in high-density lipoproteins subclasses. Am J Obstet 1983; 145:446–452.
15. Wahl P, Walden C, Knopp R, Hoover J, Wallace R, Heiss G, Rifkind B. Effect of estrogen/progestin potency on lipid/lipoprotein cholesterol. N Engl J Med 1983; 308:862–867.
16. Wynn V, Niththyananthan R. The effect of progestin in combined oral contraceptives on serum lipids with special reference to high density lipoproteins. Am J Obstet Gynecol 1982;142:766–771.
17. Wynn V, Godsland I. Effects of oral contraceptives on carbohydrate metabolism. J Reprod Med 1986;31(9)(Supplement):892–897.
18. LaRosa JC. Atherosclerotic risk factors in cardiovascular disease. J Reprod Med 1986;31(9)(Supplement):906–912.
19. Inman WH, Vessey MP. Investigation of death from pulmonary, coronary, and cerebral thrombosis and embolism in women of child-bearing age. Br Med J 1968;2(5599):193–199.
20. Maguire MG, Tonascia J, Sartwell PE, Stolley PD, Tockman MS. Increased risk of thrombosis due to oral contraceptives: a further report. Am J Epidemiol 1979;110(2):188–195.
21. Petitti DB, Wingerd J, Pellegrin F, Ramacharan S. Risk of vascular disease in women: smoking, oral contraceptives, noncontraceptive estrogens, and other factors. JAMA 1979;242:1150–1154.
22. Vessey MP, Doll R, Investigation of relation between use of oral contraceptives and thromboembolic disease. Br Med J 1968;2(5599):199–205.
23. Vessey MP, Doll R. Investigation of relation between use of oral contraceptives and thromboembolic disease. A further report. Br Med J 1969; 2(5658):651–657.
24. Porter JB, Hunter JR, Danielson DA, Jick H, Stergachis A. Oral contraceptives and non-fatal vascular disease - recent experience. Obstet Gynecol 1982;59(3):299–302.
25. Vessey M, Doll R, Peto R, Johnson B, Wiggins P. A long-term follow-up study of women using different methods of contraception: an interim report. J Biosocial Sci 1976;8:375–427.
26. Royal College of General Practitioners: Oral Contraceptives, venous thrombosis, and varicose veins. J Royal Coll Gen Pract 1978; 28:393–399.
27. Collaborative Group for the Study of Stroke in Young Women: Oral contraception and increased risk of cerebral ischemia or thrombosis. N Engl J Med 1973;288:871–878.
28. Petitti DB, Wingerd J. Use of oral contraceptives, cigarette smoking, and risk of subarachnoid hemorrhage. Lancet 1978;2:234–236.
29. Inman WH. Oral contraceptives and fatal subarachnoid hemorrhage. Br Med J 1979:2(6203):1468–1470.
30. Collaborative Group for the Study of Stroke in Young Women: Oral Contraceptives and stroke in young women: associated risk factors. JAMA 1975; 231:718–722.
31. Inman WH, Vessey MP, Westerholm B, Engelund A. Thromboembolic disease and the steroidal content of oral contraceptives. A report to the Committee on Safety of Drugs. Br Med J 1970;2:203–209.
32. Meade TW, Greenberg G, Thompson SG. Progestogens and cardiovascular reactions associated with oral contraceptives and a comparison of the safety of 50- and 35-mcg oestrogen preparations. Br Med J 1980;280(6224):1157–1161.
33. Kay CR. Progestogens and arterial disease - evidence from the Royal College of General Practitioners' Study. Am J Obstet Gynecol 1982;142:762–765.
34. Royal College of General Practitioners: Incidence of arterial disease among oral contraceptive users. J Royal Coll Gen Pract 1983;33:75–82.
35. Ory HW. Mortality associated with fertility and fertility control: 1983. Family Planning Perspectives 1983;15:50–56.
36. The Cancer and Steroid Hormone Study of the Centers for Disease Control and the National Institute of Child Health and Human Development: Oral contraceptive use and the risk of breast cancer. N Engl J Med 1986;315:405–411.
37. Pike MC, Henderson BE, Krailo MD, Duke A, Roy S. Breast cancer in young women and use of oral contraceptives: possible modifying effect of formulation and age at use. Lancet 1983;2:926–929.
38. Paul C, Skegg DG, Spears GFS, Kaldor JM. Oral contraceptives and breast cancer: A national study. Br Med J 1986; 293:723–725.
39. Miller DR, Rosenberg L, Kaufman DW, Schottenfeld D, Stolley PD, Shapiro S. Breast cancer risk in relation to early oral contraceptive use. Obstet Gynecol 1986;68:863–868.
40. Olsson H, Olsson ML, Moller TR, Ranstam J, Holm P. Oral contraceptive use and breast cancer in young women in Sweden (letter). Lancet 1985; 1(8431):748–749.
41. McPherson K, Vessey M, Neil A, Doll R, Jones L, Roberts M. Early contraceptive use and breast cancer: Results of another case-control study. Br J Cancer 1987; 56:653–660.
42. Huggins GR, Zucker PF. Oral contraceptives and neoplasia; 1987 update. Fertil Steril 1987; 47:733–761.
43. McPherson K, Drife JO. The pill and breast cancer: why the uncertainty? Br Med J 1986; 293:709–710.
44. Shapiro S. Oral contraceptives - time to take stock. N Engl J Med 1987; 315:450–451.
45. Ory H, Naib Z, Conger SB, Hatcher RA, Tyler CW. Contraceptive choice and prevalence of cervical dysplasia and carcinoma in situ. Am J Obstet Gynecol 1976; 124:573–577.
46. Vessey MP, Lawless M, McPherson K, Yeates D. Neoplasia of the cervix uteri and contraception: a possible adverse effect of the pill. Lancet 1983; 2:930.
47. Brinton LA, Huggins GR, Lehman HF, Malli K, Savitz DA, Trapido E, Rosenthal J, Hoover R. Long term use of oral contraceptives and risk of invasive cervical cancer. Int J Cancer 1986; 38:339–344.
48. WHO Collaborative Study of Neoplasia and Steroid Contraceptives: Invasive cervical cancer and combined oral contraceptives. Br Med J 1985; 290:961–965.
49. Rooks JB, Ory HW, Ishak KG, Strauss LT, Greenspan JR, Hill AP, Tyler CW. Epidemiology of hepatocellular adenoma: the role of oral contraceptive use. JAMA 1979; 242:644–648.
50. Bein NN, Goldsmith HS. Recurrent massive hemorrhage from benign hepatic tumors secondary to oral contraceptives. Br J Surg 1977; 64:433–435.
51. Klatskin G. Hepatic tumors: possible relationship to use of oral contraceptives. Gastroenterology 1977; 73:386–394.
52. Henderson BE, Preston-Martin S, Edmondson HA, Peters RL, Pike MC. Hepatocellular carcinoma and oral contraceptives. Br J Cancer 1983;48:437–440.
53. Neuberger J, Forman D, Doll R, Williams R. Oral contraceptives and hepatocellular carcinoma. Br Med J 1986; 292:1355–1357.
54. Forman D, Vincent TJ, Doll R, Cancer of the liver and oral contraceptives. Br Med J 1986; 292:1357–1361.
55. Harlap S, Eldor J. Births following oral contraceptive failures. Obstet Gynecol 1980; 55:447–452.
56. Savolainen E, Saksela E, Saxen L. Teratogenic hazards of oral contraceptives analyzed in a national malformation register. Am J Obstet Gynecol 1981: 140:521–524.
57. Janerich DT, Piper JM, Glebatis DM. Oral contraceptives and birth defects. Am J Epidemiol 1980; 112:73–79.
58. Ferencz C, Matanoski GM, Wilson PD, Rubin JD, Neill CA, Gutberlet R. Maternal hormone therapy and congenital heart disease. Teratology 1980; 21:225–239.
59. Rothman KJ, Fyler DC, Goldblatt A, Kreidberg MB. Exogenous hormones and other drug exposures of children with congenital heart disease. Am J Epidemiol 1979; 109:433–439.
60. Boston Collaborative Drug Surveillance Program: Oral contraceptives and venous thromboembolic disease, surgically confirmed gallbladder disease, and breast tumors. Lancet 1973; 1:1399–1404.
61. Royal College of General Practitioners: Oral contraceptives and health. New York, Pittman 1974.
62. Layde PM, Vessey MP, Yeates D. Risk of gallbladder disease: a cohort study of young women attending family planning clinics. J Epidemiol Community Health 1982; 36:274–278.
63. Rome Group for Epidemiology and Prevention of Cholelithiasis (GREPCO): Prevalence of gallstone disease in an Italian adult female population. Am J Epidemiol 1984; 119:796–805.
64. Storm BL, Tamragouri RT, Morse ML, Lazar EL, West SL, Stolley PD, Jones JK. Oral contraceptives and other risk factors for gallbladder disease. Clin Pharmacol Ther 1986; 39:335–341.
65. Wynn V, Adams PW, Godsland IF, Melrose J, Niththyananthan R, Oakley NW, Seedj A. Comparison of effects of different combined oral contraceptive formulations on carbohydrate and lipid metabolism. Lancet 1979; 1:1045–1049.
66. Wynn V. Effect of progesterone and progestins on carbohydrate metabolism. In: Progesterone and Progestin. Bardin CW, Milgrom E, Mauvis-Jarvis P. eds. New York, Raven Press 1983; pp. 395–410.
67. Perlman JA, Roussell-Briefel RG, Ezzati TM, Lieberknecht G. Oral glucose tolerance and the potency of oral contraceptive progestogens. J Chronic Dis 1985;38:857–864.
68. Royal College of General Practitioners' Oral Contraception Study: Effect on hypertension and benign breast disease of progestogen component in combined oral contraceptives. Lancet 1977; 1:624.
69. Fisch IR, Frank J. Oral contraceptives and blood pressure. JAMA 1977; 237:2499–2503.
70. Laragh AJ. Oral contraceptive induced hypertension-nine years later. Am J Obstet Gynecol 1976; 126:141–147.
71. Ramcharan S, Peritz E, Pellegrin FA, Williams WT. Incidence of hypertension in the Walnut Creek Contraceptive Drug Study cohort: In: Pharmacology of steroid contraceptive drugs. Garattini S, Berendes HW. Eds. New York, Raven Press, 1977; pp. 277–288, (Monographs of the Mario Negri Institute for Pharmacological Research Milan.)
72. Stockley I. Interactions with oral contraceptives. J Pharm 1976;216:140–143.
73. The Cancer and Steroid Hormone Study of the Centers for Disease Control and the National Institute of Child Health and Human Development: Oral contraceptive use and the risk of ovarian cancer. JAMA 1983; 249:1596–1599.
74. The Cancer and Steroid Hormone Study of the Centers for Disease Control and the National Institute of Child Health and Human Development: Combination oral contraceptive use and the risk of endometrial cancer. JAMA 1987; 257:796–800.
75. Ory HW. Functional ovarian cysts and oral contraceptives: negative association confirmed surgically. JAMA 1974; 228:68–69.
76. Ory HW, Cole P, MacMahon B, Hoover R. Oral contraceptives and reduced risk of benign breast disease. N Engl J Med 1976; 294:419–422.
77. Ory HW. The noncontraceptive health benefits from oral contraceptive use. Fam Plann Perspect 1982; 14:182–184.
78. Ory HW, Forrest JD, Lincoln R. Making choices: Evaluating the health risks and benefits of birth control methods. New York, The Alan Guttmacher Institute, 1983; p.1.
79. Schlesselman J, Stadel BV, Murray P, Lai S. Breast cancer in relation to early use of oral contraceptives. JAMA 1988; 259:1828–1833.
80. Hennekens CH, Speizer FE, Lipnick RJ, Rosner B, Bain C, Belanger C, Stampfer MJ, Willett W, Peto R. A case-control study of oral contraceptive use and breast cancer. JNCI 1984; 72:39–42.
81. LaVecchia C, Decarli A, Fasoli M, Franceschi S, Gentile A, Negri E, Parazzini F, Tognoni G. Oral contraceptives and cancers of the breast and of the female genital tract. Interim results from a case-control study. Br J Cancer 1986; 54:311–317.
82. Meirik O, Lund E, Adami H, Bergstrom R, Christoffersen T, Bergsjo P. Oral contraceptive use and breast cancer in young women. A Joint National Case-control study in Sweden and Norway. Lancet 1986; 11:650–654.
83. Kay CR, Hannaford PC. Breast cancer and the pill - A further report from the Royal College of General Practitioners' oral contraception study. Br J Cancer 1988;58:675–680.
84. Stadel BV, Lai S, Schlesselman JJ, Murray P. Oral contraceptives and premenopausal breast cancer in nulliparous women. Contraception 1988; 38:287–299.
85. Miller DR, Rosenberg L, Kaufman DW, Stolley P, Warshauer ME, Shapiro S. Breast cancer before age 45 and oral contraceptive use: New Findings. Am J Epidemiol 1989; 129:269–280.
86. The UK National Case-Control Study Group, Oral contraceptive use and breast cancer risk in young women. Lancet 1989; 1:973–982.
87. Schlesselman JJ. Cancer of the breast and reproductive tract in relation to use of oral contraceptives. Contraception 1989; 40:1–38.
88. Vessey MP, McPherson K, Villard-Mackintosh L, Yeates D. Oral contraceptives and breast cancer: latest findings in a large cohort study. Br J Cancer 1989; 59:613–617.
89. Jick SS, Walker AM, Stergachis A, Jick H. Oral contraceptives and breast cancer. Br J Cancer 1989; 59:618–621.
90. Anderson FD, Selectivity and minimal androgenicity of norgestimate in monophasic and triphasic oral contraceptives. Acta Obstet Gynecol Scand 1992; 156 (Supplement):15–21.
91. Chapdelaine A, Desmaris J-L, Derman RJ. Clinical evidence of minimal androgenic activity of norgestimate. Int J Fertil 1989; 34(51):347–352.
92. Phillips A, Demarest K, Hahn DW, Wong F, McGuire JL. Progestational and androgenic receptor binding affinities and in vivo activities of norgestimate and other progestins. Contraception 1989; 41(4):399–409.
93. Phillips A, Hahn DW, Klimek S, McGuire JL. A comparison of the potencies and activities of progestogens used in contraceptives. Contraception 1987; 36(2):181–192.
94. Janaud A, Rouffy J, Upmalis D, Dain M-P. A comparison study of lipid and androgen metabolism with triphasic oral contraceptive formulations containing norgestimate or levonorgestrel. Acta Obstet Gynecol Scand 1992; 156 (Supplement):34–38.
95. Collaborative Group on Hormonal Factors in Breast Cancer. Breast cancer and hormonal contraceptives: collaborative reanalysis of individual data on 53,297 women with breast cancer and 100,239 women without breast cancer from 54 epidemiological studies. Lancet 1996; 347:1713–1727.
96. Palmer JR, Rosenberg L, Kaufman DW, Warshauer ME, Stolley P, Shapiro S. Oral Contraceptive Use and Liver Cancer. Am J Epidemiol 1989;130:878–882.
97. Lewis M, Spitzer WO, Heinemann LAJ, MacRae KD, Bruppacher R, Thorogood M on behalf of Transnational Research Group on Oral Contraceptives and Health of Young Women. Third generation oral contraceptives and risk of myocardial infarction: an international case-control study. Br Med J, 1996;312:88–90.
98. Improving access to quality care in family planning: Medical eligibility criteria for contraceptive use. Geneva, WHO, Family and Reproductive Health, 1996.
99. Hampton RM, Short M, Bieber E, et al. Comparison of a novel norgestimate/ethinyl estradiol oral contraceptive (Ortho Tri-Cyclen Lo) with the oral contraceptive Loestrin Fe 1/20. Contraception 2001;63:289–295.
100. Sitteri PK, Murai JT, Hammond GL, Nisker JA, Raymoure WJ, Huhn RW. The serum transport of steroid hormones. Rec Prog Horm Res 1982;38:457–510.
101. Bork K, Fischer B, DeWald G. Recurrent episodes of skin angioedema and severe attacks of abdominal pain induced by oral contraceptives or hormone replacement therapy. Am J Med 2003;114:294–298.
102. Van Giersbergen PLM, Halabi A, Dingemanse J. Pharmacokinetic interaction between bosentan and the oral contraceptives norethisterone and ethinyl estradiol. Int J Clin Pharmacol Ther 2006;44(3):113–118.
103. Christensen J, Petrenaite V, Atterman J, et al. Oral contraceptives induce lamotrigine metabolism: evidence from a double-blind, placebo-controlled trial. Epilepsia 2007;48(3):484–489.

BRIEF SUMMARY PATIENT PACKAGE INSERT

Oral contraceptives, also known as "birth control pills" or "the pill," are taken to prevent pregnancy. When taken correctly without missing any pills, oral contraceptives are highly effective; however the typical failure rate of large numbers of pill users is 5% per year when women who miss pills are included. Forgetting to take pills considerably increases the chances of pregnancy. For most women oral contraceptives are also free of serious or unpleasant side effects.

For the majority of women, oral contraceptives can be taken safely. But there are some women who are at high risk of developing certain serious diseases that can be fatal or may cause temporary or permanent disability. The risks associated with taking oral contraceptives increase significantly if you:

- smoke
- have high blood pressure, diabetes, high cholesterol
- have or have had clotting disorders, heart attack, stroke, angina pectoris, cancer of the breast or sex organs, jaundice or malignant or benign liver tumors

Although cardiovascular disease risks may be increased with oral contraceptive use after age 40 in healthy, non-smoking women (even with the newer low-dose formulations), there are also greater potential health risks associated with pregnancy in older women.

You should not take the pill if you suspect you are pregnant or have unexplained vaginal bleeding.

BOXED WARNING

Cigarette smoking increases the risk of serious cardiovascular side effects from oral contraceptive use. This risk increases with age and with heavy smoking (15 or more cigarettes per day) and is quite marked in women over 35 years of age. Women who use oral contraceptives are strongly advised not to smoke.

Most side effects of the pill are not serious. The most common such effects are nausea, vomiting, bleeding between menstrual periods, weight gain, breast tenderness, and difficulty wearing contact lenses. These side effects, especially nausea and vomiting, may subside within the first three months of use.

The serious side effects of the pill occur very infrequently, especially if you are in good health and are young. However, you should know that the following medical conditions have been associated with or made worse by the pill:

1. Blood clots in the legs (thrombophlebitis), lungs (pulmonary embolism), stoppage or rupture of a blood vessel in the brain (stroke), blockage of blood vessels in the heart (heart attack or angina pectoris) or other organs of the body. As mentioned above, smoking increases the risk of heart attacks and strokes and subsequent serious medical consequences.
2. In rare cases, oral contraceptives can cause benign but dangerous liver tumors. These benign liver tumors can rupture and cause fatal internal bleeding. In addition, some studies report an increased risk of developing liver cancer. However, liver cancers are rare.
3. High blood pressure, although blood pressure usually returns to normal when the pill is stopped.

The symptoms associated with these serious side effects are discussed in the detailed leaflet given to you with your supply of pills. Notify your healthcare professional if you notice any unusual physical disturbances while taking the pill. In addition, drugs such as rifampin, bosentan, as well as some anti-convulsants and some antibiotics, and herbal preparations containing St. John's Wort (hypericum perforatum) may decrease oral contraceptive effectiveness.

Oral contraceptives may interact with lamotrigine (LAMICTAL®), an anticonvulsant used for epilepsy. This may increase the risk of seizures so your healthcare professional may need to adjust the dose of lamotrigine.

Various studies give conflicting reports on the relationship between breast cancer and oral contraceptive use. Oral contraceptive use may slightly increase your chance of having breast cancer diagnosed, particularly after using hormonal contraceptives at a younger age. After you stop using hormonal contraceptives, the chances of having breast cancer diagnosed begin to go back down. You should have regular breast examinations by a healthcare professional and examine your own breasts monthly. Tell your healthcare professional if you have a family history of breast cancer or if you have had breast nodules or an abnormal mammogram. Women who currently have or have had breast cancer should not use oral contraceptives because breast cancer is usually a hormone-sensitive tumor.

Some studies have found an increase in the incidence of cancer of the cervix in women who use oral contraceptives. However, this finding may be related to factors other than the use of oral contraceptives. There is insufficient evidence to rule out the possibility that the pill may cause such cancers.

Taking the combination pill provides some important non-contraceptive benefits. These include less painful menstruation, less menstrual blood loss and anemia, fewer pelvic infections, and fewer cancers of the ovary and the lining of the uterus.

Be sure to discuss any medical condition you may have with your healthcare professional. Your healthcare professional will take a medical and family history before prescribing oral contraceptives and will examine you. The physical examination may be delayed to another time if you request it and the healthcare professional believes that it is a good medical practice to postpone it. You should be reexamined at least once a year while taking oral contraceptives. Your pharmacist should have given you the detailed patient information labeling which gives you further information which you should read and discuss with your healthcare professional.

ORTHO TRI-CYCLEN® Lo (like all oral contraceptives) is intended to prevent pregnancy. Oral contraceptives do not protect against transmission of HIV (AIDS) and other sexually transmitted diseases such as chlamydia, genital herpes, genital warts, gonorrhea, hepatitis B, and syphilis.

HOW TO TAKE THE PILL

IMPORTANT POINTS TO REMEMBER

BEFORE YOU START TAKING YOUR PILLS:

1. BE SURE TO READ THESE DIRECTIONS:
  Before you start taking your pills.
  Anytime you are not sure what to do.
2. THE RIGHT WAY TO TAKE THE PILL IS TO TAKE ONE PILL EVERY DAY AT THE SAME TIME.
  If you miss pills you could get pregnant. This includes starting the pack late.
  The more pills you miss, the more likely you are to get pregnant.
3. MANY WOMEN HAVE SPOTTING OR LIGHT BLEEDING, OR MAY FEEL SICK TO THEIR STOMACH DURING THE FIRST 1–3 PACKS OF PILLS. If you feel sick to your stomach, do not stop taking the pill. The problem will usually go away. If it doesn't go away, check with your healthcare professional.
4. MISSING PILLS CAN ALSO CAUSE SPOTTING OR LIGHT BLEEDING, even when you make up these missed pills.
  On the days you take 2 pills to make up for missed pills, you could also feel a little sick to your stomach.
5. IF YOU HAVE VOMITING OR DIARRHEA, or IF YOU TAKE SOME MEDICINES, including some antibiotics, your pills may not work as well.
  Use a back-up method (such as a condom or spermicide) until you check with your healthcare professional.
6. IF YOU HAVE TROUBLE REMEMBERING TO TAKE THE PILL, talk to your healthcare professional about how to make pill-taking easier or about using another method of birth control.
7. IF YOU HAVE ANY QUESTIONS OR ARE UNSURE ABOUT THE INFORMATION IN THIS LEAFLET, call your healthcare professional.

BEFORE YOU START TAKING YOUR PILLS

1. DECIDE WHAT TIME OF DAY YOU WANT TO TAKE YOUR PILL.
  It is important to take it at about the same time every day.
2. The 28-pill pack has 21 white, light blue, and dark blue "active" pills (with hormones) to take for 3 weeks. This is followed by 1 week of dark green "reminder" pills (without hormones).
3. ALSO FIND:
  1) where on the pack to start taking pills,
  2) in what order to take the pills.

CHECK PICTURE OF PILL PACK AND ADDITIONAL INSTRUCTIONS FOR USING THIS PACKAGE IN THE BRIEF SUMMARY PATIENT PACKAGE INSERT.

4. BE SURE YOU HAVE READY AT ALL TIMES:
  ANOTHER KIND OF BIRTH CONTROL (such as a condom or spermicide) to use as a back-up method in case you miss pills.
  AN EXTRA, FULL PILL PACK.

WHEN TO START THE FIRST PACK OF PILLS

You have a choice of which day to start taking your first pack of pills. ORTHO TRI-CYCLEN® Lo is available with the DIALPAK® Tablet Dispenser which is preset for a Sunday Start. Day 1 Start is also provided. Decide with your healthcare professional which is the best day for you. Pick a time of day that will be easy to remember.

Sunday Start:

Take the first white "active" pill of the first pack on the Sunday after your period starts, even if you are still bleeding. If your period begins on Sunday, start the pack that same day.

Use another method of birth control (such as a condom or spermicide) as a back-up method if you have sex anytime from the Sunday you start your first pack until the next Sunday (7 days).

Day 1 Start:

Take the first white "active" pill of the first pack during the first 24 hours of your period.

You will not need to use a back-up method of birth control, since you are starting the pill at the beginning of your period.

WHAT TO DO DURING THE MONTH

1. Take One Pill At The Same Time Every Day Until The Pack Is Empty
  Do not skip pills even if you are spotting or bleeding between monthly periods or feel sick to your stomach (nausea).
  Do not skip pills even if you do not have sex very often.
2. When You Finish A Pack Or Switch Your Brand Of Pills
  Start the next pack on the day after your last dark green "reminder" pill. Do not wait any days between packs.

WHAT TO DO IF YOU MISS PILLS

If you MISS 1 white, light blue or dark blue "active" pill:

1. Take it as soon as you remember. Take the next pill at your regular time. This means you may take 2 pills in 1 day.
2. You do not need to use a back-up birth control method if you have sex.

If you MISS 2 white or light blue "active" pills in a row in WEEK 1 OR WEEK 2 of your pack:

1. Take 2 pills on the day you remember and 2 pills the next day.
2. Then take 1 pill a day until you finish the pack.
3. You COULD BECOME PREGNANT if you have sex in the 7 days after you miss pills. You MUST use another birth control method (such as a condom or spermicide) as a back-up method for those 7 days.

If you MISS 2 dark blue "active" pills in a row in THE 3RD WEEK:

1. If you are a Sunday Starter:
  Keep taking 1 pill every day until Sunday. On Sunday, THROW OUT the rest of the pack and start a new pack of pills that same day.
  If you are a Day 1 Starter:
  THROW OUT the rest of the pill pack and start a new pack that same day.
2. You may not have your period this month but this is expected. However, if you miss your period 2 months in a row, call your healthcare professional because you might be pregnant.
3. You COULD BECOME PREGNANT if you have sex in the 7 days after you miss pills. You MUST use another birth control method (such as a condom or spermicide) as a back-up method for those 7 days.

If you MISS 3 OR MORE white, light blue or dark blue "active" pills in a row (during the first 3 weeks):

1. If you are a Sunday Starter:
  Keep taking 1 pill every day until Sunday. On Sunday, THROW OUT the rest of the pack and start a new pack of pills that same day.
  If you are a Day 1 Starter:
  THROW OUT the rest of the pill pack and start a new pack that same day.
2. You may not have your period this month but this is expected. However, if you miss your period 2 months in a row, call your healthcare professional because you might be pregnant.
3. You COULD BECOME PREGNANT if you have sex in the 7 days after you miss pills. You MUST use another birth control method (such as a condom or spermicide) as a back-up method for those 7 days.

If you forget any of the 7 dark green "reminder" pills in Week 4:

THROW AWAY the pills you missed.

Keep taking 1 pill each day until the pack is empty.

You do not need a back-up method.

FINALLY, IF YOU ARE STILL NOT SURE WHAT TO DO ABOUT THE PILLS YOU HAVE MISSED:

Use a BACK-UP METHOD anytime you have sex.

KEEP TAKING ONE "ACTIVE" PILL EACH DAY until you can reach your healthcare professional.

DETAILED PATIENT LABELING

PLEASE NOTE: This labeling is revised from time to time as important new medical information becomes available. Therefore, please review this labeling carefully.

ORTHO TRI-CYCLEN® Lo Tablets

Each white tablet contains 0.180 mg norgestimate and 0.025 mg ethinyl estradiol.

Each light blue tablet contains 0.215 mg norgestimate and 0.025 mg ethinyl estradiol.

Each dark blue tablet contains 0.250 mg norgestimate and 0.025 mg ethinyl estradiol.

Each dark green tablet contains inert ingredients.

INTRODUCTION

Any woman who considers using oral contraceptives (the birth control pill or the pill) should understand the benefits and risks of using this form of birth control. This patient labeling will give you much of the information you will need to make this decision and will also help you determine if you are at risk of developing any of the serious side effects of the pill. It will tell you how to use the pill properly so that it will be as effective as possible. However, this labeling is not a replacement for a careful discussion between you and your healthcare professional. You should discuss the information provided in this labeling with him or her, both when you first start taking the pill and during your revisits. You should also follow your healthcare professional's advice with regard to regular check-ups while you are on the pill.

EFFECTIVENESS OF ORAL CONTRACEPTIVES FOR CONTRACEPTION

Oral contraceptives or "birth control pills" or "the pill" are used to prevent pregnancy and are more effective than most other non-surgical methods of birth control. When taken correctly without missing any pills, oral contraceptives are highly effective; however, typical failure rates are 5% per year. The chance of becoming pregnant increases with each missed pill during a menstrual cycle.

In comparison, typical failure rates for other non-surgical methods of birth control during the first year of use are as follows:

Implant: <1%

Injection: <1%

IUD: 1 to 2%

Diaphragm with spermicides: 20%

Spermicides alone: 26%

Vaginal sponge: 20 to 40%

Female sterilization: <1%

Male sterilization: <1%

Cervical Cap with spermicide: 20 to 40%

Condom alone (male): 14%

Condom alone (female): 21%

Periodic abstinence: 25%

No methods: 85%

Withdrawal: 19%

WHO SHOULD NOT TAKE ORAL CONTRACEPTIVES

BOXED WARNING

Cigarette smoking increases the risk of serious cardiovascular side effects from oral contraceptive use. This risk increases with age and with heavy smoking (15 or more cigarettes per day) and is quite marked in women over 35 years of age. Women who use oral contraceptives are strongly advised not to smoke.

Some women should not use the pill. You should not use the pill if you have any of the following conditions:

- A history of heart attack or stroke
- Blood clots in the legs (thrombophlebitis), lungs (pulmonary embolism), or eyes
- A history of blood clots in the deep veins of your legs
- Chest pain (angina pectoris)
- Known or suspected breast cancer or cancer of the lining of the uterus, cervix or vagina
- Unexplained vaginal bleeding (until a diagnosis is reached by your healthcare professional)
- Yellowing of the whites of the eyes or of the skin (jaundice) during pregnancy or during previous use of the pill
- Liver tumor (benign or cancerous)
- Known or suspected pregnancy
- If you plan to have surgery with prolonged bed rest

Tell your healthcare professional if you have ever had any of these conditions. Your healthcare professional can recommend a safer method of birth control.

OTHER CONSIDERATIONS BEFORE TAKING ORAL CONTRACEPTIVES

Tell your healthcare professional if you have or have had:

- Breast nodules, fibrocystic disease of the breast, an abnormal breast x-ray or mammogram
- Diabetes
- Elevated cholesterol or triglycerides
- High blood pressure
- Migraine or other headaches or epilepsy
- Mental depression
- Gallbladder, liver, heart or kidney disease
- History of scanty or irregular menstrual periods

Women with any of these conditions should be checked often by their healthcare professional if they choose to use oral contraceptives.

Also, be sure to inform your healthcare professional if you smoke or are on any medications.

RISKS OF TAKING ORAL CONTRACEPTIVES

1. Risk of Developing Blood Clots

Blood clots and blockage of blood vessels are one of the most serious side effects of taking oral contraceptives and can cause death or serious disability. In particular, a clot in the legs can cause thrombophlebitis and a clot that travels to the lungs can cause a sudden blocking of the vessel carrying blood to the lungs. Rarely, clots occur in the blood vessels of the eye and may cause blindness, double vision, or impaired vision.

If you take oral contraceptives and need elective surgery, need to stay in bed for a prolonged illness or injury or have recently delivered a baby, you may be at risk of developing blood clots. You should consult your healthcare professional about stopping oral contraceptives four weeks before surgery and not taking oral contraceptives for two weeks after surgery or during bed rest. You should also not take oral contraceptives soon after delivery of a baby. It is advisable to wait for at least four weeks after delivery if you are not breastfeeding. If you are breastfeeding, you should wait until you have weaned your child before using the pill. (See also the section on Breastfeeding in General Precautions.)

The risk of circulatory disease in oral contraceptive users may be higher in users of high-dose pills and may be greater with longer duration of oral contraceptive use. In addition, some of these increased risks may continue for a number of years after stopping oral contraceptives. The risk of abnormal blood clotting increases with age in both users and nonusers of oral contraceptives, but the increased risk from the oral contraceptive appears to be present at all ages. For women aged 20 to 44 it is estimated that about 1 in 2,000 using oral contraceptives will be hospitalized each year because of abnormal clotting. Among nonusers in the same age group, about 1 in 20,000 would be hospitalized each year. For oral contraceptive users in general, it has been estimated that in women between the ages of 15 and 34 the risk of death due to a circulatory disorder is about 1 in 12,000 per year, whereas for nonusers the rate is about 1 in 50,000 per year. In the age group 35 to 44, the risk is estimated to be about 1 in 2,500 per year for oral contraceptive users and about 1 in 10,000 per year for nonusers.

2. Heart Attacks and Strokes

Oral contraceptives may increase the tendency to develop strokes (stoppage or rupture of blood vessels in the brain) and angina pectoris and heart attacks (blockage of blood vessels in the heart). Any of these conditions can cause death or serious disability.

Smoking greatly increases the possibility of suffering heart attacks and strokes. Furthermore, smoking and the use of oral contraceptives greatly increase the chances of developing and dying of heart disease.

3. Gallbladder Disease

Oral contraceptive users probably have a greater risk than nonusers of having gallbladder disease, although this risk may be related to pills containing high doses of estrogens.

4. Liver Tumors

In rare cases, oral contraceptives can cause benign but dangerous liver tumors. These benign liver tumors can rupture and cause fatal internal bleeding. In addition, some studies report an increased risk of developing liver cancer. However, liver cancers are rare.

5. Cancer of the Reproductive Organs and Breasts

Various studies give conflicting reports on the relationship between breast cancer and oral contraceptive use. Oral contraceptive use may slightly increase your chance of having breast cancer diagnosed, particularly after using hormonal contraceptives at a younger age. After you stop using hormonal contraceptives, the chances of having breast cancer diagnosed begin to go back down. You should have regular breast examinations by a healthcare professional and examine your own breasts monthly. Tell your healthcare professional if you have a family history of breast cancer or if you have had breast nodules or an abnormal mammogram. Women who currently have or have had breast cancer should not use oral contraceptives because breast cancer is usually a hormone-sensitive tumor.

Some studies have found an increase in the incidence of cancer of the cervix in women who use oral contraceptives. However, this finding may be related to factors other than the use of oral contraceptives. There is insufficient evidence to rule out the possibility that the pill may cause such cancers.

ESTIMATED RISK OF DEATH FROM A BIRTH CONTROL METHOD OR PREGNANCY

All methods of birth control and pregnancy are associated with a risk of developing certain diseases which may lead to disability or death. An estimate of the number of deaths associated with different methods of birth control and pregnancy has been calculated and is shown in the following table.

Table 4: Annual Number of Birth-Related or Method-Related Deaths Associated with Control of Fertility per 100,000 Nonsterile Women, by Fertility-Control Method and According to Age
Method of control and outcome | 15–19 | 20–24 | 25–29 | 30–34 | 35–39 | 40–44
No fertility-control methods [Deaths are birth-related] | 7.0 | 7.4 | 9.1 | 14.8 | 25.7 | 28.2
Oral contraceptives, non-smoker [Deaths are method-related] | 0.3 | 0.5 | 0.9 | 1.9 | 13.8 | 31.6
Oral contraceptives, smoker | 2.2 | 3.4 | 6.6 | 13.5 | 51.1 | 117.2
IUD | 0.8 | 0.8 | 1.0 | 1.0 | 1.4 | 1.4
Condom | 1.1 | 1.6 | 0.7 | 0.2 | 0.3 | 0.4
Diaphragm/spermicide | 1.9 | 1.2 | 1.2 | 1.3 | 2.2 | 2.8
Periodic abstinence | 2.5 | 1.6 | 1.6 | 1.7 | 2.9 | 3.6
Adapted from H.W. Ory, Family Planning Perspectives, Ref. #35.

In the above table, the risk of death from any birth control method is less than the risk of childbirth, except for oral contraceptive users over the age of 35 who smoke and pill users over the age of 40 even if they do not smoke. It can be seen in the table that for women aged 15 to 39, the risk of death was highest with pregnancy (7–26 deaths per 100,000 women, depending on age). Among pill users who do not smoke, the risk of death was always lower than that associated with pregnancy for any age group, although over the age of 40, the risk increases to 32 deaths per 100,000 women, compared to 28 associated with pregnancy at that age. However, for pill users who smoke and are over the age of 35, the estimated number of deaths exceeds those for other methods of birth control. If a woman is over the age of 40 and smokes, her estimated risk of death is four times higher (117/100,000 women) than the estimated risk associated with pregnancy (28/100,000 women) in that age group.

The suggestion that women over 40 who do not smoke should not take oral contraceptives is based on information from older, higher-dose pills. An Advisory Committee of the FDA discussed this issue in 1989 and recommended that the benefits of low-dose oral contraceptive use by healthy, non-smoking women over 40 years of age may outweigh the possible risks. Older women, as all women, who take oral contraceptives, should take an oral contraceptive which contains the least amount of estrogen and progestogen that is compatible with the individual patient needs.

WARNING SIGNALS

If any of these adverse effects occur while you are taking oral contraceptives, call your healthcare professional immediately:

- Sharp chest pain, coughing of blood, or sudden shortness of breath (indicating a possible clot in the lung)
- Pain in the calf (indicating a possible clot in the leg)
- Crushing chest pain or heaviness in the chest (indicating a possible heart attack)
- Sudden severe headache or vomiting, dizziness or fainting, disturbances of vision or speech, weakness, or numbness in an arm or leg (indicating a possible stroke)
- Sudden partial or complete loss of vision (indicating a possible clot in the eye)
- Breast lumps (indicating possible breast cancer or fibrocystic disease of the breast; ask your healthcare professional to show you how to examine your breasts)
- Severe pain or tenderness in the stomach area (indicating a possibly ruptured liver tumor)
- Difficulty in sleeping, weakness, lack of energy, fatigue, or change in mood (possibly indicating severe depression)
- Jaundice or a yellowing of the skin or eyeballs, accompanied frequently by fever, fatigue, loss of appetite, dark colored urine, or light colored bowel movements (indicating possible liver problems)

SIDE EFFECTS OF ORAL CONTRACEPTIVES

1. Vaginal Bleeding

Irregular vaginal bleeding or spotting may occur while you are taking the pills. Irregular bleeding may vary from slight staining between menstrual periods to breakthrough bleeding which is a flow much like a regular period. Irregular bleeding occurs most often during the first few months of oral contraceptive use, but may also occur after you have been taking the pill for some time. Such bleeding may be temporary and usually does not indicate any serious problems. It is important to continue taking your pills on schedule. If the bleeding occurs in more than one cycle or lasts for more than a few days, talk to your healthcare professional.

2. Contact Lenses

If you wear contact lenses and notice a change in vision or an inability to wear your lenses, contact your healthcare professional.

3. Fluid Retention

Oral contraceptives may cause edema (fluid retention) with swelling of the fingers or ankles and may raise your blood pressure. If you experience fluid retention, contact your healthcare professional.

4. Melasma

A spotty darkening of the skin is possible, particularly of the face, which may persist.

5. Other Side Effects

Other side effects may include nausea and vomiting, change in appetite, headache, nervousness, depression, dizziness, loss of scalp hair, rash, vaginal infections, and allergic reactions.

If any of these side effects bother you, call your healthcare professional.

GENERAL PRECAUTIONS

1. Missed Periods and Use of Oral Contraceptives Before or During Early Pregnancy

There may be times when you may not menstruate regularly after you have completed taking a cycle of pills. If you have taken your pills regularly and miss one menstrual period, continue taking your pills for the next cycle but be sure to inform your healthcare professional. If you have not taken the pills daily as instructed and missed a menstrual period, you may be pregnant. If you missed two consecutive menstrual periods, you may be pregnant. Check with your healthcare professional immediately to determine whether you are pregnant. Stop taking oral contraceptives if pregnancy is confirmed.

There is no conclusive evidence that oral contraceptive use is associated with an increase in birth defects, when taken inadvertently during early pregnancy. Previously, a few studies had reported that oral contraceptives might be associated with birth defects, but these findings have not been seen in more recent studies. Nevertheless, oral contraceptives should not be used during pregnancy. You should check with your healthcare professional about risks to your unborn child of any medication taken during pregnancy.

2. While Breastfeeding

If you are breastfeeding, consult your healthcare professional before starting oral contraceptives. Some of the drug will be passed on to the child in the milk. A few adverse effects on the child have been reported, including yellowing of the skin (jaundice) and breast enlargement. In addition, oral contraceptives may decrease the amount and quality of your milk. If possible, do not use oral contraceptives while breastfeeding. You should use another method of contraception since breastfeeding provides only partial protection from becoming pregnant and this partial protection decreases significantly as you breastfeed for longer periods of time. You should consider starting oral contraceptives only after you have weaned your child completely.

3. Laboratory Tests

If you are scheduled for any laboratory tests, tell your healthcare professional you are taking birth control pills. Certain blood tests may be affected by birth control pills.

4. Drug Interactions

Certain drugs may interact with birth control pills to make them less effective in preventing pregnancy or cause an increase in breakthrough bleeding. Such drugs include rifampin, drugs used for epilepsy such as barbiturates (for example, phenobarbital), topiramate (TOPAMAX®), carbamazepine (Tegretol® is one brand of this drug), or phenytoin (Dilantin® is one brand of this drug); phenylbutazone (Butazolidin® is one brand); certain drugs used in the treatment of HIV or AIDS; and possibly certain antibiotics. Medicine for pulmonary hypertension, such as bosentan (Tracleer®). Pregnancies and breakthrough bleeding have been reported by women who also used some form of the herbal supplement St. John's Wort while using combined hormonal contraceptives. Hormonal contraceptives may interact with lamotrigine (LAMICTAL®), an anticonvulsant used for epilepsy. This may increase the risk of seizures so your healthcare professional may need to adjust the dose of lamotrigine. You may need to use additional contraception when you take other products which can make oral contraceptives less effective. Be sure to tell your healthcare professional if you are taking or start taking any medications while taking birth control pills.

5. Sexually Transmitted Diseases

ORTHO TRI-CYCLEN® Lo (like all oral contraceptives) is intended to prevent pregnancy. Oral contraceptives do not protect against transmission of HIV (AIDS) and other sexually transmitted diseases such as chlamydia, genital herpes, genital warts, gonorrhea, hepatitis B, and syphilis.

HOW TO TAKE THE PILL

IMPORTANT POINTS TO REMEMBER

BEFORE YOU START TAKING YOUR PILLS:

1. BE SURE TO READ THESE DIRECTIONS:
  Before you start taking your pills.
  Anytime you are not sure what to do.
2. THE RIGHT WAY TO TAKE THE PILL IS TO TAKE ONE PILL EVERY DAY AT THE SAME TIME.
  If you miss pills you could get pregnant. This includes starting the pack late.
  The more pills you miss, the more likely you are to get pregnant.
3. MANY WOMEN HAVE SPOTTING OR LIGHT BLEEDING, OR MAY FEEL SICK TO THEIR STOMACH DURING THE FIRST 1–3 PACKS OF PILLS. If you feel sick to your stomach, do not stop taking the pill. The problem will usually go away. If it doesn't go away, check with your healthcare professional.
4. MISSING PILLS CAN ALSO CAUSE SPOTTING OR LIGHT BLEEDING, even when you make up these missed pills.
  On the days you take 2 pills to make up for missed pills, you could also feel a little sick to your stomach.
5. IF YOU HAVE VOMITING OR DIARRHEA, or IF YOU TAKE SOME MEDICINES, including some antibiotics, your pills may not work as well.
  Use a back-up method (such as a condom or spermicide) until you check with your healthcare professional.
6. IF YOU HAVE TROUBLE REMEMBERING TO TAKE THE PILL, talk to your healthcare professional about how to make pill-taking easier or about using another method of birth control.
7. IF YOU HAVE ANY QUESTIONS OR ARE UNSURE ABOUT THE INFORMATION IN THIS LEAFLET, call your healthcare professional.

BEFORE YOU START TAKING YOUR PILLS

1. DECIDE WHAT TIME OF DAY YOU WANT TO TAKE YOUR PILL.
  It is important to take it at about the same time every day.
2. The pill pack has 21 white, light blue, and dark blue "active" pills (with hormones) to take for 3 weeks. This is followed by 1 week of dark green "reminder" pills (without hormones).
3. ALSO FIND:
  1) where on the pack to start taking pills,
  2) in what order to take the pills.

CHECK PICTURE OF PILL PACK AND ADDITIONAL INSTRUCTIONS FOR USING THIS PACKAGE IN THE BRIEF SUMMARY PATIENT PACKAGE INSERT.

4. BE SURE YOU HAVE READY AT ALL TIMES:
  ANOTHER KIND OF BIRTH CONTROL (such as a condom or spermicide) to use as a back-up method in case you miss pills.
  AN EXTRA, FULL PILL PACK.

WHEN TO START THE FIRST PACK OF PILLS

You have a choice of which day to start taking your first pack of pills. ORTHO TRI-CYCLEN® Lo is available with the DIALPAK® Tablet Dispenser which is preset for a Sunday Start. Day 1 Start is also provided. Decide with your healthcare professional which is the best day for you. Pick a time of day that will be easy to remember.

Sunday Start:

Take the first white "active" pill of the first pack on the Sunday after your period starts, even if you are still bleeding. If your period begins on Sunday, start the pack that same day.

Use another method of birth control (such as a condom or spermicide) as a back-up method if you have sex anytime from the Sunday you start your first pack until the next Sunday (7 days).

Day 1 Start:

Take the first white "active" pill of the first pack during the first 24 hours of your period.

You will not need to use a back-up method of birth control, since you are starting the pill at the beginning of your period.

WHAT TO DO DURING THE MONTH

1. Take One Pill At The Same Time Every Day Until The Pack Is Empty
  Do not skip pills even if you are spotting or bleeding between monthly periods or feel sick to your stomach (nausea).
  Do not skip pills even if you do not have sex very often.
2. When You Finish A Pack Or Switch Your Brand Of Pills
  Start the next pack on the day after your last dark green "reminder" pill. Do not wait any days between packs.

WHAT TO DO IF YOU MISS PILLS

If you MISS 1 white, light blue or dark blue "active" pill:

1. Take it as soon as you remember. Take the next pill at your regular time. This means you may take 2 pills in 1 day.
2. You do not need to use a back-up birth control method if you have sex.

If you MISS 2 white or light blue "active" pills in a row in WEEK 1 OR WEEK 2 of your pack:

1. Take 2 pills on the day you remember and 2 pills the next day.
2. Then take 1 pill a day until you finish the pack.
3. You COULD BECOME PREGNANT if you have sex in the 7 days after you miss pills. You MUST use another birth control method (such as a condom or spermicide) as a back-up method for those 7 days.

If you MISS 2 dark blue "active" pills in a row in THE 3RD WEEK:

1. If you are a Sunday Starter:
  Keep taking 1 pill every day until Sunday. On Sunday, THROW OUT the rest of the pack and start a new pack of pills that same day.
  If you are a Day 1 Starter:
  THROW OUT the rest of the pill pack and start a new pack that same day.
2. You may not have your period this month but this is expected. However, if you miss your period 2 months in a row, call your healthcare professional because you might be pregnant.
3. You COULD BECOME PREGNANT if you have sex in the 7 days after you miss pills. You MUST use another birth control method (such as a condom or spermicide) as a back-up method for those 7 days.

If you MISS 3 OR MORE white, light blue or dark blue "active" pills in a row (during the first 3 weeks):

1. If you are a Sunday Starter:
  Keep taking 1 pill every day until Sunday. On Sunday, THROW OUT the rest of the pack and start a new pack of pills that same day.
  If you are a Day 1 Starter:
  THROW OUT the rest of the pill pack and start a new pack that same day.
2. You may not have your period this month but this is expected. However, if you miss your period 2 months in a row, call your healthcare professional because you might be pregnant.
3. You COULD BECOME PREGNANT if you have sex in the 7 days after you miss pills. You MUST use another birth control method (such as a condom or spermicide) as a back-up method for those 7 days.

If you forget any of the 7 dark green "reminder" pills in Week 4:

THROW AWAY the pills you missed.

Keep taking 1 pill each day until the pack is empty.

You do not need a back-up method.

FINALLY, IF YOU ARE STILL NOT SURE WHAT TO DO ABOUT THE PILLS YOU HAVE MISSED:

Use a BACK-UP METHOD anytime you have sex.

KEEP TAKING ONE "ACTIVE" PILL EACH DAY until you can reach your healthcare professional.

PREGNANCY DUE TO PILL FAILURE

When taken correctly without missing any pills, oral contraceptives are highly effective; however the typical failure rate of large numbers of pill users is 5% per year when women who miss pills are included. If failure does occur, the risk to the fetus is minimal.

PREGNANCY AFTER STOPPING THE PILL

There may be some delay in becoming pregnant after you stop using oral contraceptives, especially if you had irregular menstrual cycles before you used oral contraceptives. It may be advisable to postpone conception until you begin menstruating regularly once you have stopped taking the pill and desire pregnancy.

There does not appear to be any increase in birth defects in newborn babies when pregnancy occurs soon after stopping the pill.

OVERDOSAGE

Serious ill effects have not been reported following ingestion of large doses of oral contraceptives by young children. Overdosage may cause nausea and withdrawal bleeding in females. In case of overdosage, contact your healthcare professional or pharmacist.

OTHER INFORMATION

Your healthcare professional will take a medical and family history before prescribing oral contraceptives and will examine you. The physical examination may be delayed to another time if you request it and the healthcare professional believes that it is a good medical practice to postpone it. You should be reexamined at least once a year. Be sure to inform your healthcare professional if there is a family history of any of the conditions listed previously in this leaflet. Be sure to keep all appointments with your healthcare professional because this is a time to determine if there are early signs of side effects of oral contraceptive use.

Do not use the drug for any condition other than the one for which it was prescribed. This drug has been prescribed specifically for you; do not give it to others who may want birth control pills.

HEALTH BENEFITS FROM ORAL CONTRACEPTIVES

In addition to preventing pregnancy, use of combination oral contraceptives may provide certain benefits. They are:

- menstrual cycles may become more regular
- blood flow during menstruation may be lighter and less iron may be lost. Therefore, anemia due to iron deficiency is less likely to occur
- pain or other symptoms during menstruation may be encountered less frequently
- ectopic (tubal) pregnancy may occur less frequently
- noncancerous cysts or lumps in the breast may occur less frequently
- acute pelvic inflammatory disease may occur less frequently
- oral contraceptive use may provide some protection against developing two forms of cancer: cancer of the ovaries and cancer of the lining of the uterus

If you want more information about birth control pills, ask your healthcare professional or pharmacist. They have a more technical leaflet called the Professional Labeling, which you may wish to read. The professional labeling is also published in a book entitled Physicians' Desk Reference, available in many bookstores and public libraries.

Mfd. for:

Ortho Women's Health & Urology, Division of Ortho-McNeil-Janssen Pharmaceuticals, Inc.

Raritan, New Jersey 08869

Mfd. by:

Janssen Ortho, LLC

Manati, Puerto Rico 00674

© Ortho-McNeil-Janssen Pharmaceuticals, Inc. 1998

Revised June 2010

10213500

Relabeling "Additional barcode label" by:
Physicians Total Care, Inc.
Tulsa, OK 74146

PRINCIPAL DISPLAY PANEL

28
day

NDC 54868-4730-0

ORTHO
TRI~CYCLEN® LO
(norgestimate/ethinyl estradiol)
TABLETS

Special
Offer
Inside!

Each white tablet contains 0.180 mg norgestimate and 0.025 mg ethinyl
estradiol. Each light blue tablet contains 0.215 mg norgestimate and 0.025 mg
ethinyl estradiol. Each dark blue tablet contains 0.250 mg norgestimate and
0.025 mg ethinyl estradiol. Each green tablet contains inert ingredients.

Rx only.

Store at 25°C (77°F); excursions permitted to 15° - 30°C
(59° - 86°F). Protect from light.